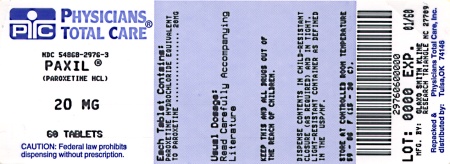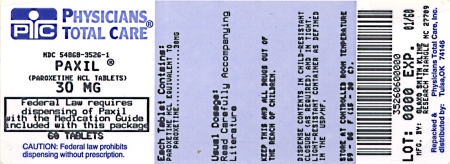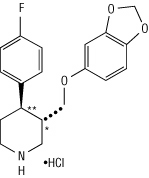 DRUG LABEL: PAXIL
NDC: 54868-2976 | Form: TABLET, FILM COATED
Manufacturer: Physicians Total Care, Inc.
Category: prescription | Type: HUMAN PRESCRIPTION DRUG LABEL
Date: 20120105

ACTIVE INGREDIENTS: PAROXETINE HYDROCHLORIDE 20 mg/1 1
INACTIVE INGREDIENTS: DIBASIC CALCIUM PHOSPHATE DIHYDRATE; HYPROMELLOSES; MAGNESIUM STEARATE; POLYSORBATE 80; SODIUM STARCH GLYCOLATE TYPE A POTATO; TITANIUM DIOXIDE

PAXIL®
(paroxetine hydrochloride) Tablets and Oral Suspension

Suicidality and Antidepressant Drugs

Antidepressants increased the risk compared to placebo of suicidal thinking and behavior (suicidality) in children, adolescents, and young adults in short-term studies of major depressive disorder (MDD) and other psychiatric disorders. Anyone considering the use of PAXIL or any other antidepressant in a child, adolescent, or young adult must balance this risk with the clinical need. Short-term studies did not show an increase in the risk of suicidality with antidepressants compared to placebo in adults beyond age 24; there was a reduction in risk with antidepressants compared to placebo in adults aged 65 and older. Depression and certain other psychiatric disorders are themselves associated with increases in the risk of suicide. Patients of all ages who are started on antidepressant therapy should be monitored appropriately and observed closely for clinical worsening, suicidality, or unusual changes in behavior. Families and caregivers should be advised of the need for close observation and communication with the prescriber. PAXIL is not approved for use in pediatric patients. (See WARNINGS: Clinical Worsening and Suicide Risk, PRECAUTIONS: Information for Patients, and PRECAUTIONS: Pediatric Use.)

DESCRIPTION

PAXIL (paroxetine hydrochloride) is an orally administered psychotropic drug. It is the hydrochloride salt of a phenylpiperidine compound identified chemically as (-)-trans-4R-(4'-fluorophenyl)-3S-[(3',4'-methylenedioxyphenoxy) methyl] piperidine hydrochloride hemihydrate and has the empirical formula of C19H20FNO3•HCl•1/2H2O. The molecular weight is 374.8 (329.4 as free base). The structural formula of paroxetine hydrochloride is:

Paroxetine hydrochloride is an odorless, off-white powder, having a melting point range of 120° to 138°C and a solubility of 5.4 mg/mL in water.

Tablets

Each film-coated tablet contains paroxetine hydrochloride equivalent to paroxetine as follows: 10 mg–yellow (scored); 20 mg–pink (scored); 30 mg–blue, 40 mg–green. Inactive ingredients consist of dibasic calcium phosphate dihydrate, hypromellose, magnesium stearate, polyethylene glycols, polysorbate 80, sodium starch glycolate, titanium dioxide, and 1 or more of the following: D&C Red No. 30 aluminum lake, D&C Yellow No. 10 aluminum lake, FD&C Blue No. 2 aluminum lake, FD&C Yellow No. 6 aluminum lake.

Suspension for Oral Administration

Each 5 mL of orange-colored, orange-flavored liquid contains paroxetine hydrochloride equivalent to paroxetine, 10 mg. Inactive ingredients consist of polacrilin potassium, microcrystalline cellulose, propylene glycol, glycerin, sorbitol, methylparaben, propylparaben, sodium citrate dihydrate, citric acid anhydrous, sodium saccharin, flavorings, FD&C Yellow No. 6 aluminum lake, and simethicone emulsion, USP.

CLINICAL PHARMACOLOGY

Pharmacodynamics

The efficacy of paroxetine in the treatment of major depressive disorder, social anxiety disorder, obsessive compulsive disorder (OCD), panic disorder (PD), generalized anxiety disorder (GAD), and posttraumatic stress disorder (PTSD) is presumed to be linked to potentiation of serotonergic activity in the central nervous system resulting from inhibition of neuronal reuptake of serotonin (5-hydroxy-tryptamine, 5-HT). Studies at clinically relevant doses in humans have demonstrated that paroxetine blocks the uptake of serotonin into human platelets. In vitro studies in animals also suggest that paroxetine is a potent and highly selective inhibitor of neuronal serotonin reuptake and has only very weak effects on norepinephrine and dopamine neuronal reuptake. In vitro radioligand binding studies indicate that paroxetine has little affinity for muscarinic, alpha1-, alpha2-, beta-adrenergic-, dopamine (D2)-, 5-HT1-, 5-HT2-, and histamine (H1)-receptors; antagonism of muscarinic, histaminergic, and alpha1-adrenergic receptors has been associated with various anticholinergic, sedative, and cardiovascular effects for other psychotropic drugs.

Because the relative potencies of paroxetine’s major metabolites are at most 1/50 of the parent compound, they are essentially inactive.

Pharmacokinetics

Paroxetine hydrochloride is completely absorbed after oral dosing of a solution of the hydrochloride salt. The mean elimination half-life is approximately 21 hours (CV 32%) after oral dosing of 30 mg tablets of PAXIL daily for 30 days. Paroxetine is extensively metabolized and the metabolites are considered to be inactive. Nonlinearity in pharmacokinetics is observed with increasing doses. Paroxetine metabolism is mediated in part by CYP2D6, and the metabolites are primarily excreted in the urine and to some extent in the feces. Pharmacokinetic behavior of paroxetine has not been evaluated in subjects who are deficient in CYP2D6 (poor metabolizers).

In a meta-analysis of paroxetine from 4 studies done in healthy volunteers following multiple dosing of 20 mg/day to 40 mg/day, males did not exhibit a significantly lower Cmax or AUC than females.

Absorption and Distribution

Paroxetine is equally bioavailable from the oral suspension and tablet.

Paroxetine hydrochloride is completely absorbed after oral dosing of a solution of the hydrochloride salt. In a study in which normal male subjects (n = 15) received 30 mg tablets daily for 30 days, steady-state paroxetine concentrations were achieved by approximately 10 days for most subjects, although it may take substantially longer in an occasional patient. At steady state, mean values of Cmax, Tmax, Cmin, and T½ were 61.7 ng/mL (CV 45%), 5.2 hr. (CV 10%), 30.7 ng/mL (CV 67%), and 21.0 hours (CV 32%), respectively. The steady-state Cmax and Cmin values were about 6 and 14 times what would be predicted from single-dose studies. Steady-state drug exposure based on AUC0-24 was about 8 times greater than would have been predicted from single-dose data in these subjects. The excess accumulation is a consequence of the fact that 1 of the enzymes that metabolizes paroxetine is readily saturable.

The effects of food on the bioavailability of paroxetine were studied in subjects administered a single dose with and without food. AUC was only slightly increased (6%) when drug was administered with food but the Cmax was 29% greater, while the time to reach peak plasma concentration decreased from 6.4 hours post-dosing to 4.9 hours.

Paroxetine distributes throughout the body, including the CNS, with only 1% remaining in the plasma.

Approximately 95% and 93% of paroxetine is bound to plasma protein at 100 ng/mL and 400 ng/mL, respectively. Under clinical conditions, paroxetine concentrations would normally be less than 400 ng/mL. Paroxetine does not alter the in vitro protein binding of phenytoin or warfarin.

Metabolism and Excretion

The mean elimination half-life is approximately 21 hours (CV 32%) after oral dosing of 30 mg tablets daily for 30 days of PAXIL. In steady-state dose proportionality studies involving elderly and nonelderly patients, at doses of 20 mg to 40 mg daily for the elderly and 20 mg to 50 mg daily for the nonelderly, some nonlinearity was observed in both populations, again reflecting a saturable metabolic pathway. In comparison to Cmin values after 20 mg daily, values after 40 mg daily were only about 2 to 3 times greater than doubled.

Paroxetine is extensively metabolized after oral administration. The principal metabolites are polar and conjugated products of oxidation and methylation, which are readily cleared. Conjugates with glucuronic acid and sulfate predominate, and major metabolites have been isolated and identified. Data indicate that the metabolites have no more than 1/50 the potency of the parent compound at inhibiting serotonin uptake. The metabolism of paroxetine is accomplished in part by CYP2D6. Saturation of this enzyme at clinical doses appears to account for the nonlinearity of paroxetine kinetics with increasing dose and increasing duration of treatment. The role of this enzyme in paroxetine metabolism also suggests potential drug-drug interactions (see PRECAUTIONS: Drugs Metabolized by CYP2D6).

Approximately 64% of a 30-mg oral solution dose of paroxetine was excreted in the urine with 2% as the parent compound and 62% as metabolites over a 10-day post-dosing period. About 36% was excreted in the feces (probably via the bile), mostly as metabolites and less than 1% as the parent compound over the 10-day post-dosing period.

Other Clinical Pharmacology Information

Specific Populations

Renal and Liver Disease

Increased plasma concentrations of paroxetine occur in subjects with renal and hepatic impairment. The mean plasma concentrations in patients with creatinine clearance below 30 mL/min. were approximately 4 times greater than seen in normal volunteers. Patients with creatinine clearance of 30 to 60 mL/min. and patients with hepatic functional impairment had about a 2-fold increase in plasma concentrations (AUC, Cmax).

The initial dosage should therefore be reduced in patients with severe renal or hepatic impairment, and upward titration, if necessary, should be at increased intervals (see DOSAGE AND ADMINISTRATION).

Elderly Patients

In a multiple-dose study in the elderly at daily paroxetine doses of 20, 30, and 40 mg, Cmin concentrations were about 70% to 80% greater than the respective Cmin concentrations in nonelderly subjects. Therefore the initial dosage in the elderly should be reduced (see DOSAGE AND ADMINISTRATION).

Drug-Drug Interactions

In vitro drug interaction studies reveal that paroxetine inhibits CYP2D6. Clinical drug interaction studies have been performed with substrates of CYP2D6 and show that paroxetine can inhibit the metabolism of drugs metabolized by CYP2D6 including desipramine, risperidone, and atomoxetine (see PRECAUTIONS: Drug Interactions).

Major Depressive Disorder

The efficacy of PAXIL as a treatment for major depressive disorder has been established in 6 placebo-controlled studies of patients with major depressive disorder (aged 18 to 73). In these studies, PAXIL was shown to be significantly more effective than placebo in treating major depressive disorder by at least 2 of the following measures: Hamilton Depression Rating Scale (HDRS), the Hamilton depressed mood item, and the Clinical Global Impression (CGI)-Severity of Illness. PAXIL was significantly better than placebo in improvement of the HDRS sub-factor scores, including the depressed mood item, sleep disturbance factor, and anxiety factor.

A study of outpatients with major depressive disorder who had responded to PAXIL (HDRS total score <8) during an initial 8-week open-treatment phase and were then randomized to continuation on PAXIL or placebo for 1 year demonstrated a significantly lower relapse rate for patients taking PAXIL (15%) compared to those on placebo (39%). Effectiveness was similar for male and female patients.

Obsessive Compulsive Disorder

The effectiveness of PAXIL in the treatment of obsessive compulsive disorder (OCD) was demonstrated in two 12-week multicenter placebo-controlled studies of adult outpatients (Studies 1 and 2). Patients in all studies had moderate to severe OCD (DSM-IIIR) with mean baseline ratings on the Yale Brown Obsessive Compulsive Scale (YBOCS) total score ranging from 23 to 26. Study 1, a dose-range finding study where patients were treated with fixed doses of 20, 40, or 60 mg of paroxetine/day demonstrated that daily doses of paroxetine 40 and 60 mg are effective in the treatment of OCD. Patients receiving doses of 40 and 60 mg paroxetine experienced a mean reduction of approximately 6 and 7 points, respectively, on the YBOCS total score which was significantly greater than the approximate 4-point reduction at 20 mg and a 3-point reduction in the placebo-treated patients. Study 2 was a flexible-dose study comparing paroxetine (20 to 60 mg daily) with clomipramine (25 to 250 mg daily). In this study, patients receiving paroxetine experienced a mean reduction of approximately 7 points on the YBOCS total score, which was significantly greater than the mean reduction of approximately 4 points in placebo-treated patients.

The following table provides the outcome classification by treatment group on Global Improvement items of the Clinical Global Impression (CGI) scale for Study 1.

Outcome Classification (%) on CGI-Global Improvement Item
for Completers in Study 1
Outcome; Classification | Placebo; (n = 74) | PAXIL 20 mg; (n = 75) | PAXIL 40 mg; (n = 66) | PAXIL 60 mg; (n = 66)
Worse | 14% | 7% | 7% | 3%
No Change | 44% | 35% | 22% | 19%
Minimally Improved | 24% | 33% | 29% | 34%
Much Improved | 11% | 18% | 22% | 24%
Very Much Improved | 7% | 7% | 20% | 20%

Subgroup analyses did not indicate that there were any differences in treatment outcomes as a function of age or gender.

The long-term maintenance effects of PAXIL in OCD were demonstrated in a long-term extension to Study 1. Patients who were responders on paroxetine during the 3-month double-blind phase and a 6-month extension on open-label paroxetine (20 to 60 mg/day) were randomized to either paroxetine or placebo in a 6-month double-blind relapse prevention phase. Patients randomized to paroxetine were significantly less likely to relapse than comparably treated patients who were randomized to placebo.

Panic Disorder

The effectiveness of PAXIL in the treatment of panic disorder was demonstrated in three 10- to 12-week multicenter, placebo-controlled studies of adult outpatients (Studies 1-3). Patients in all studies had panic disorder (DSM-IIIR), with or without agoraphobia. In these studies, PAXIL was shown to be significantly more effective than placebo in treating panic disorder by at least 2 out of 3 measures of panic attack frequency and on the Clinical Global Impression Severity of Illness score.

Study 1 was a 10-week dose-range finding study; patients were treated with fixed paroxetine doses of 10, 20, or 40 mg/day or placebo. A significant difference from placebo was observed only for the 40 mg/day group. At endpoint, 76% of patients receiving paroxetine 40 mg/day were free of panic attacks, compared to 44% of placebo-treated patients.

Study 2 was a 12-week flexible-dose study comparing paroxetine (10 to 60 mg daily) and placebo. At endpoint, 51% of paroxetine patients were free of panic attacks compared to 32% of placebo-treated patients.

Study 3 was a 12-week flexible-dose study comparing paroxetine (10 to 60 mg daily) to placebo in patients concurrently receiving standardized cognitive behavioral therapy. At endpoint, 33% of the paroxetine-treated patients showed a reduction to 0 or 1 panic attacks compared to 14% of placebo patients.

In both Studies 2 and 3, the mean paroxetine dose for completers at endpoint was approximately 40 mg/day of paroxetine.

Long-term maintenance effects of PAXIL in panic disorder were demonstrated in an extension to Study 1. Patients who were responders during the 10-week double-blind phase and during a 3-month double-blind extension phase were randomized to either paroxetine (10, 20, or 40 mg/day) or placebo in a 3-month double-blind relapse prevention phase. Patients randomized to paroxetine were significantly less likely to relapse than comparably treated patients who were randomized to placebo.

Subgroup analyses did not indicate that there were any differences in treatment outcomes as a function of age or gender.

Social Anxiety Disorder

The effectiveness of PAXIL in the treatment of social anxiety disorder was demonstrated in three 12-week, multicenter, placebo-controlled studies (Studies 1, 2, and 3) of adult outpatients with social anxiety disorder (DSM-IV). In these studies, the effectiveness of PAXIL compared to placebo was evaluated on the basis of (1) the proportion of responders, as defined by a Clinical Global Impression (CGI) Improvement score of 1 (very much improved) or 2 (much improved), and (2) change from baseline in the Liebowitz Social Anxiety Scale (LSAS).

Studies 1 and 2 were flexible-dose studies comparing paroxetine (20 to 50 mg daily) and placebo. Paroxetine demonstrated statistically significant superiority over placebo on both the CGI Improvement responder criterion and the Liebowitz Social Anxiety Scale (LSAS). In Study 1, for patients who completed to week 12, 69% of paroxetine-treated patients compared to 29% of placebo-treated patients were CGI Improvement responders. In Study 2, CGI Improvement responders were 77% and 42% for the paroxetine- and placebo-treated patients, respectively.

Study 3 was a 12-week study comparing fixed paroxetine doses of 20, 40, or 60 mg/day with placebo. Paroxetine 20 mg was demonstrated to be significantly superior to placebo on both the LSAS Total Score and the CGI Improvement responder criterion; there were trends for superiority over placebo for the 40 mg and 60 mg/day dose groups. There was no indication in this study of any additional benefit for doses higher than 20 mg/day.

Subgroup analyses generally did not indicate differences in treatment outcomes as a function of age, race, or gender.

Generalized Anxiety Disorder

The effectiveness of PAXIL in the treatment of Generalized Anxiety Disorder (GAD) was demonstrated in two 8-week, multicenter, placebo-controlled studies (Studies 1 and 2) of adult outpatients with Generalized Anxiety Disorder (DSM-IV).

Study 1 was an 8-week study comparing fixed paroxetine doses of 20 mg or 40 mg/day with placebo. Doses of 20 mg or 40 mg of PAXIL were both demonstrated to be significantly superior to placebo on the Hamilton Rating Scale for Anxiety (HAM-A) total score. There was not sufficient evidence in this study to suggest a greater benefit for the 40 mg/day dose compared to the 20 mg/day dose.

Study 2 was a flexible-dose study comparing paroxetine (20 mg to 50 mg daily) and placebo. PAXIL demonstrated statistically significant superiority over placebo on the Hamilton Rating Scale for Anxiety (HAM-A) total score. A third study, also flexible-dose comparing paroxetine (20 mg to 50 mg daily), did not demonstrate statistically significant superiority of PAXIL over placebo on the Hamilton Rating Scale for Anxiety (HAM-A) total score, the primary outcome.

Subgroup analyses did not indicate differences in treatment outcomes as a function of race or gender. There were insufficient elderly patients to conduct subgroup analyses on the basis of age.

In a longer-term trial, 566 patients meeting DSM-IV criteria for Generalized Anxiety Disorder, who had responded during a single-blind, 8-week acute treatment phase with 20 to 50 mg/day of PAXIL, were randomized to continuation of PAXIL at their same dose, or to placebo, for up to 24 weeks of observation for relapse. Response during the single-blind phase was defined by having a decrease of ≥2 points compared to baseline on the CGI-Severity of Illness scale, to a score of ≤3. Relapse during the double-blind phase was defined as an increase of ≥2 points compared to baseline on the CGI-Severity of Illness scale to a score of ≥4, or withdrawal due to lack of efficacy. Patients receiving continued PAXIL experienced a significantly lower relapse rate over the subsequent 24 weeks compared to those receiving placebo.

Posttraumatic Stress Disorder

The effectiveness of PAXIL in the treatment of Posttraumatic Stress Disorder (PTSD) was demonstrated in two 12-week, multicenter, placebo-controlled studies (Studies 1 and 2) of adult outpatients who met DSM-IV criteria for PTSD. The mean duration of PTSD symptoms for the 2 studies combined was 13 years (ranging from .1 year to 57 years). The percentage of patients with secondary major depressive disorder or non-PTSD anxiety disorders in the combined 2 studies was 41% (356 out of 858 patients) and 40% (345 out of 858 patients), respectively. Study outcome was assessed by (i) the Clinician-Administered PTSD Scale Part 2 (CAPS-2) score and (ii) the Clinical Global Impression-Global Improvement Scale (CGI-I). The CAPS-2 is a multi-item instrument that measures 3 aspects of PTSD with the following symptom clusters: Reexperiencing/intrusion, avoidance/numbing and hyperarousal. The 2 primary outcomes for each trial were (i) change from baseline to endpoint on the CAPS-2 total score (17 items), and (ii) proportion of responders on the CGI-I, where responders were defined as patients having a score of 1 (very much improved) or 2 (much improved).

Study 1 was a 12-week study comparing fixed paroxetine doses of 20 mg or 40 mg/day to placebo. Doses of 20 mg and 40 mg of PAXIL were demonstrated to be significantly superior to placebo on change from baseline for the CAPS-2 total score and on proportion of responders on the CGI-I. There was not sufficient evidence in this study to suggest a greater benefit for the 40 mg/day dose compared to the 20 mg/day dose.

Study 2 was a 12-week flexible-dose study comparing paroxetine (20 to 50 mg daily) to placebo. PAXIL was demonstrated to be significantly superior to placebo on change from baseline for the CAPS-2 total score and on proportion of responders on the CGI-I.

A third study, also a flexible-dose study comparing paroxetine (20 to 50 mg daily) to placebo, demonstrated PAXIL to be significantly superior to placebo on change from baseline for CAPS-2 total score, but not on proportion of responders on the CGI-I.

The majority of patients in these trials were women (68% women: 377 out of 551 subjects in Study 1 and 66% women: 202 out of 303 subjects in Study 2). Subgroup analyses did not indicate differences in treatment outcomes as a function of gender. There were an insufficient number of patients who were 65 years and older or were non-Caucasian to conduct subgroup analyses on the basis of age or race, respectively.

INDICATIONS AND USAGE

Major Depressive Disorder

PAXIL is indicated for the treatment of major depressive disorder.

The efficacy of PAXIL in the treatment of a major depressive episode was established in 6-week controlled trials of outpatients whose diagnoses corresponded most closely to the DSM-III category of major depressive disorder (see CLINICAL PHARMACOLOGY: Clinical Trials). A major depressive episode implies a prominent and relatively persistent depressed or dysphoric mood that usually interferes with daily functioning (nearly every day for at least 2 weeks); it should include at least 4 of the following 8 symptoms: Change in appetite, change in sleep, psychomotor agitation or retardation, loss of interest in usual activities or decrease in sexual drive, increased fatigue, feelings of guilt or worthlessness, slowed thinking or impaired concentration, and a suicide attempt or suicidal ideation.

The effects of PAXIL in hospitalized depressed patients have not been adequately studied.

The efficacy of PAXIL in maintaining a response in major depressive disorder for up to 1 year was demonstrated in a placebo-controlled trial (see CLINICAL PHARMACOLOGY: Clinical Trials). Nevertheless, the physician who elects to use PAXIL for extended periods should periodically re-evaluate the long-term usefulness of the drug for the individual patient.

Obsessive Compulsive Disorder

PAXIL is indicated for the treatment of obsessions and compulsions in patients with obsessive compulsive disorder (OCD) as defined in the DSM-IV. The obsessions or compulsions cause marked distress, are time-consuming, or significantly interfere with social or occupational functioning.

The efficacy of PAXIL was established in two 12-week trials with obsessive compulsive outpatients whose diagnoses corresponded most closely to the DSM-IIIR category of obsessive compulsive disorder (see CLINICAL PHARMACOLOGY: Clinical Trials).

Obsessive compulsive disorder is characterized by recurrent and persistent ideas, thoughts, impulses, or images (obsessions) that are ego-dystonic and/or repetitive, purposeful, and intentional behaviors (compulsions) that are recognized by the person as excessive or unreasonable.

Long-term maintenance of efficacy was demonstrated in a 6-month relapse prevention trial. In this trial, patients assigned to paroxetine showed a lower relapse rate compared to patients on placebo (see CLINICAL PHARMACOLOGY: Clinical Trials). Nevertheless, the physician who elects to use PAXIL for extended periods should periodically re-evaluate the long-term usefulness of the drug for the individual patient (see DOSAGE AND ADMINISTRATION).

Panic Disorder

PAXIL is indicated for the treatment of panic disorder, with or without agoraphobia, as defined in DSM-IV. Panic disorder is characterized by the occurrence of unexpected panic attacks and associated concern about having additional attacks, worry about the implications or consequences of the attacks, and/or a significant change in behavior related to the attacks.

The efficacy of PAXIL was established in three 10- to 12-week trials in panic disorder patients whose diagnoses corresponded to the DSM-IIIR category of panic disorder (see CLINICAL PHARMACOLOGY: Clinical Trials).

Panic disorder (DSM-IV) is characterized by recurrent unexpected panic attacks, i.e., a discrete period of intense fear or discomfort in which 4 (or more) of the following symptoms develop abruptly and reach a peak within 10 minutes: (1) palpitations, pounding heart, or accelerated heart rate; (2) sweating; (3) trembling or shaking; (4) sensations of shortness of breath or smothering; (5) feeling of choking; (6) chest pain or discomfort; (7) nausea or abdominal distress; (8) feeling dizzy, unsteady, lightheaded, or faint; (9) derealization (feelings of unreality) or depersonalization (being detached from oneself); (10) fear of losing control; (11) fear of dying; (12) paresthesias (numbness or tingling sensations); (13) chills or hot flushes.

Long-term maintenance of efficacy was demonstrated in a 3-month relapse prevention trial. In this trial, patients with panic disorder assigned to paroxetine demonstrated a lower relapse rate compared to patients on placebo (see CLINICAL PHARMACOLOGY: Clinical Trials). Nevertheless, the physician who prescribes PAXIL for extended periods should periodically re-evaluate the long-term usefulness of the drug for the individual patient (see DOSAGE AND ADMINISTRATION).

Social Anxiety Disorder

PAXIL is indicated for the treatment of social anxiety disorder, also known as social phobia, as defined in DSM-IV (300.23). Social anxiety disorder is characterized by a marked and persistent fear of 1 or more social or performance situations in which the person is exposed to unfamiliar people or to possible scrutiny by others. Exposure to the feared situation almost invariably provokes anxiety, which may approach the intensity of a panic attack. The feared situations are avoided or endured with intense anxiety or distress. The avoidance, anxious anticipation, or distress in the feared situation(s) interferes significantly with the person's normal routine, occupational or academic functioning, or social activities or relationships, or there is marked distress about having the phobias. Lesser degrees of performance anxiety or shyness generally do not require psychopharmacological treatment.

The efficacy of PAXIL was established in three 12-week trials in adult patients with social anxiety disorder (DSM-IV). PAXIL has not been studied in children or adolescents with social phobia (see CLINICAL PHARMACOLOGY: Clinical Trials).

The effectiveness of PAXIL in long-term treatment of social anxiety disorder, i.e., for more than 12 weeks, has not been systematically evaluated in adequate and well-controlled trials. Therefore, the physician who elects to prescribe PAXIL for extended periods should periodically re-evaluate the long-term usefulness of the drug for the individual patient (see DOSAGE AND ADMINISTRATION).

Generalized Anxiety Disorder

PAXIL is indicated for the treatment of Generalized Anxiety Disorder (GAD), as defined in DSM-IV. Anxiety or tension associated with the stress of everyday life usually does not require treatment with an anxiolytic.

The efficacy of PAXIL in the treatment of GAD was established in two 8-week placebo-controlled trials in adults with GAD. PAXIL has not been studied in children or adolescents with Generalized Anxiety Disorder (see CLINICAL PHARMACOLOGY: Clinical Trials).

Generalized Anxiety Disorder (DSM-IV) is characterized by excessive anxiety and worry (apprehensive expectation) that is persistent for at least 6 months and which the person finds difficult to control. It must be associated with at least 3 of the following 6 symptoms: Restlessness or feeling keyed up or on edge, being easily fatigued, difficulty concentrating or mind going blank, irritability, muscle tension, sleep disturbance.

The efficacy of PAXIL in maintaining a response in patients with Generalized Anxiety Disorder, who responded during an 8-week acute treatment phase while taking PAXIL and were then observed for relapse during a period of up to 24 weeks, was demonstrated in a placebo-controlled trial (see CLINICAL PHARMACOLOGY: Clinical Trials). Nevertheless, the physician who elects to use PAXIL for extended periods should periodically re-evaluate the long-term usefulness of the drug for the individual patient (see DOSAGE AND ADMINISTRATION).

Posttraumatic Stress Disorder

PAXIL is indicated for the treatment of Posttraumatic Stress Disorder (PTSD).

The efficacy of PAXIL in the treatment of PTSD was established in two 12-week placebo-controlled trials in adults with PTSD (DSM-IV) (see CLINICAL PHARMACOLOGY: Clinical Trials).

PTSD, as defined by DSM-IV, requires exposure to a traumatic event that involved actual or threatened death or serious injury, or threat to the physical integrity of self or others, and a response that involves intense fear, helplessness, or horror. Symptoms that occur as a result of exposure to the traumatic event include reexperiencing of the event in the form of intrusive thoughts, flashbacks, or dreams, and intense psychological distress and physiological reactivity on exposure to cues to the event; avoidance of situations reminiscent of the traumatic event, inability to recall details of the event, and/or numbing of general responsiveness manifested as diminished interest in significant activities, estrangement from others, restricted range of affect, or sense of foreshortened future; and symptoms of autonomic arousal including hypervigilance, exaggerated startle response, sleep disturbance, impaired concentration, and irritability or outbursts of anger. A PTSD diagnosis requires that the symptoms are present for at least a month and that they cause clinically significant distress or impairment in social, occupational, or other important areas of functioning.

The efficacy of PAXIL in longer-term treatment of PTSD, i.e., for more than 12 weeks, has not been systematically evaluated in placebo-controlled trials. Therefore, the physician who elects to prescribe PAXIL for extended periods should periodically re-evaluate the long-term usefulness of the drug for the individual patient (see DOSAGE AND ADMINISTRATION).

CONTRAINDICATIONS

The use of MAOIs intended to treat depression with, or within 14 days of treatment with, PAXIL is contraindicated (see WARNINGS).

Do not start PAXIL in a patient who is being treated with a reversible MAOI such as linezolid or methylene blue because of an increased risk of serotonin syndrome or neuroleptic malignant syndrome (NMS)-like reactions (see WARNINGS).

Concomitant use with thioridazine is contraindicated (see WARNINGS and PRECAUTIONS).

Concomitant use in patients taking pimozide is contraindicated (see PRECAUTIONS).

PAXIL is contraindicated in patients with a hypersensitivity to paroxetine or any of the inactive ingredients in PAXIL.

WARNINGS

Clinical Worsening and Suicide Risk

Patients with major depressive disorder (MDD), both adult and pediatric, may experience worsening of their depression and/or the emergence of suicidal ideation and behavior (suicidality) or unusual changes in behavior, whether or not they are taking antidepressant medications, and this risk may persist until significant remission occurs. Suicide is a known risk of depression and certain other psychiatric disorders, and these disorders themselves are the strongest predictors of suicide. There has been a long-standing concern, however, that antidepressants may have a role in inducing worsening of depression and the emergence of suicidality in certain patients during the early phases of treatment. Pooled analyses of short-term placebo-controlled trials of antidepressant drugs (SSRIs and others) showed that these drugs increase the risk of suicidal thinking and behavior (suicidality) in children, adolescents, and young adults (ages 18-24) with major depressive disorder (MDD) and other psychiatric disorders. Short-term studies did not show an increase in the risk of suicidality with antidepressants compared to placebo in adults beyond age 24; there was a reduction with antidepressants compared to placebo in adults aged 65 and older.

The pooled analyses of placebo-controlled trials in children and adolescents with MDD, obsessive compulsive disorder (OCD), or other psychiatric disorders included a total of 24 short-term trials of 9 antidepressant drugs in over 4,400 patients. The pooled analyses of placebo-controlled trials in adults with MDD or other psychiatric disorders included a total of 295 short-term trials (median duration of 2 months) of 11 antidepressant drugs in over 77,000 patients. There was considerable variation in risk of suicidality among drugs, but a tendency toward an increase in the younger patients for almost all drugs studied. There were differences in absolute risk of suicidality across the different indications, with the highest incidence in MDD. The risk differences (drug vs placebo), however, were relatively stable within age strata and across indications. These risk differences (drug-placebo difference in the number of cases of suicidality per 1,000 patients treated) are provided in Table 1.

Table 1.
Age Range | Drug-Placebo Difference in Number of Cases of Suicidality per 1,000 Patients Treated
Increases Compared to Placebo
<18 | 14 additional cases
18-24 | 5 additional cases
Decreases Compared to Placebo
25-64 | 1 fewer case
≥65 | 6 fewer cases

No suicides occurred in any of the pediatric trials. There were suicides in the adult trials, but the number was not sufficient to reach any conclusion about drug effect on suicide.

It is unknown whether the suicidality risk extends to longer-term use, i.e., beyond several months. However, there is substantial evidence from placebo-controlled maintenance trials in adults with depression that the use of antidepressants can delay the recurrence of depression.

All patients being treated with antidepressants for any indication should be monitored appropriately and observed closely for clinical worsening, suicidality, and unusual changes in behavior, especially during the initial few months of a course of drug therapy, or at times of dose changes, either increases or decreases.

The following symptoms, anxiety, agitation, panic attacks, insomnia, irritability, hostility, aggressiveness, impulsivity, akathisia (psychomotor restlessness), hypomania, and mania, have been reported in adult and pediatric patients being treated with antidepressants for major depressive disorder as well as for other indications, both psychiatric and nonpsychiatric. Although a causal link between the emergence of such symptoms and either the worsening of depression and/or the emergence of suicidal impulses has not been established, there is concern that such symptoms may represent precursors to emerging suicidality.

Consideration should be given to changing the therapeutic regimen, including possibly discontinuing the medication, in patients whose depression is persistently worse, or who are experiencing emergent suicidality or symptoms that might be precursors to worsening depression or suicidality, especially if these symptoms are severe, abrupt in onset, or were not part of the patient’s presenting symptoms.

If the decision has been made to discontinue treatment, medication should be tapered, as rapidly as is feasible, but with recognition that abrupt discontinuation can be associated with certain symptoms (see PRECAUTIONS and DOSAGE AND ADMINISTRATION: Discontinuation of Treatment With PAXIL, for a description of the risks of discontinuation of PAXIL).

Families and caregivers of patients being treated with antidepressants for major depressive disorder or other indications, both psychiatric and nonpsychiatric, should be alerted about the need to monitor patients for the emergence of agitation, irritability, unusual changes in behavior, and the other symptoms described above, as well as the emergence of suicidality, and to report such symptoms immediately to healthcare providers. Such monitoring should include daily observation by families and caregivers. Prescriptions for PAXIL should be written for the smallest quantity of tablets consistent with good patient management, in order to reduce the risk of overdose.

Screening Patients for Bipolar Disorder

A major depressive episode may be the initial presentation of bipolar disorder. It is generally believed (though not established in controlled trials) that treating such an episode with an antidepressant alone may increase the likelihood of precipitation of a mixed/manic episode in patients at risk for bipolar disorder. Whether any of the symptoms described above represent such a conversion is unknown. However, prior to initiating treatment with an antidepressant, patients with depressive symptoms should be adequately screened to determine if they are at risk for bipolar disorder; such screening should include a detailed psychiatric history, including a family history of suicide, bipolar disorder, and depression. It should be noted that PAXIL is not approved for use in treating bipolar depression.

Potential for Interaction With Monoamine Oxidase Inhibitors

In patients receiving another serotonin reuptake inhibitor drug in combination with monoamine oxidase inhibitors (MAOIs), including reversible MAOIs such as linezolid and methylene blue, there have been reports of serious, sometimes fatal, reactions including hyperthermia, rigidity, myoclonus, autonomic instability with possible rapid fluctuations of vital signs, and mental status changes that include extreme agitation progressing to delirium and coma. These reactions have also been reported in patients who have recently discontinued that drug and have been started on an MAOI. Some cases presented with features resembling serotonin syndrome or NMS-like reactions (see CONTRAINDICATIONS and DOSAGE AND ADMINISTRATION).

Serotonin Syndrome or Neuroleptic Malignant Syndrome (NMS)-like Reactions

The development of a potentially life-threatening serotonin syndrome or Neuroleptic Malignant Syndrome (NMS)-like reactions have been reported with SNRIs and SSRIs alone, including treatment with PAXIL, but particularly with concomitant use of serotonergic drugs (including triptans) with drugs which impair metabolism of serotonin (including MAOIs), or with antipsychotics or other dopamine antagonists. Serotonin syndrome symptoms may include mental status changes (e.g., agitation, hallucinations, coma), autonomic instability (e.g., tachycardia, labile blood pressure, hyperthermia), neuromuscular aberrations (e.g., hyperreflexia, incoordination) and/or gastrointestinal symptoms (e.g., nausea, vomiting, diarrhea). Serotonin syndrome, in its most severe form can resemble neuroleptic malignant syndrome, which includes hyperthermia, muscle rigidity, autonomic instability with possible rapid fluctuation of vital signs, and mental status changes. Patients should be monitored for the emergence of serotonin syndrome or NMS-like signs and symptoms.

The concomitant use of PAXIL with MAOIs intended to treat depression is contraindicated.

If concomitant treatment of PAXIL with a 5-hydroxytryptamine receptor agonist (triptan) is clinically warranted, careful observation of the patient is advised, particularly during treatment initiation and dose increases.

The concomitant use of PAXIL with serotonin precursors (such as tryptophan) is not recommended.

Treatment with PAXIL and any concomitant serotonergic or antidopaminergic agents, including antipsychotics, should be discontinued immediately if the above events occur and supportive symptomatic treatment should be initiated.

Potential Interaction With Thioridazine

Thioridazine administration alone produces prolongation of the QTc interval, which is associated with serious ventricular arrhythmias, such as torsade de pointes–type arrhythmias, and sudden death. This effect appears to be dose related.

An in vivo study suggests that drugs which inhibit CYP2D6, such as paroxetine, will elevate plasma levels of thioridazine. Therefore, it is recommended that paroxetine not be used in combination with thioridazine (see CONTRAINDICATIONS and PRECAUTIONS).

Usage in Pregnancy

Teratogenic Effects

Epidemiological studies have shown that infants exposed to paroxetine in the first trimester of pregnancy have an increased risk of congenital malformations, particularly cardiovascular malformations. The findings from these studies are summarized below:

- A study based on Swedish national registry data demonstrated that infants exposed to paroxetine during pregnancy (n = 815) had an increased risk of cardiovascular malformations (2% risk in paroxetine-exposed infants) compared to the entire registry population (1% risk), for an odds ratio (OR) of 1.8 (95% confidence interval 1.1 to 2.8). No increase in the risk of overall congenital malformations was seen in the paroxetine-exposed infants. The cardiac malformations in the paroxetine-exposed infants were primarily ventricular septal defects (VSDs) and atrial septal defects (ASDs). Septal defects range in severity from those that resolve spontaneously to those which require surgery.

- A separate retrospective cohort study from the United States (United Healthcare data) evaluated 5,956 infants of mothers dispensed antidepressants during the first trimester (n = 815 for paroxetine). This study showed a trend towards an increased risk for cardiovascular malformations for paroxetine (risk of 1.5%) compared to other antidepressants (risk of 1%), for an OR of 1.5 (95% confidence interval 0.8 to 2.9). Of the 12 paroxetine-exposed infants with cardiovascular malformations, 9 had VSDs. This study also suggested an increased risk of overall major congenital malformations including cardiovascular defects for paroxetine (4% risk) compared to other (2% risk) antidepressants (OR 1.8; 95% confidence interval 1.2 to 2.8).

- Two large case-control studies using separate databases, each with >9,000 birth defect cases and >4,000 controls, found that maternal use of paroxetine during the first trimester of pregnancy was associated with a 2- to 3-fold increased risk of right ventricular outflow tract obstructions. In one study the odds ratio was 2.5 (95% confidence interval, 1.0 to 6.0, 7 exposed infants) and in the other study the odds ratio was 3.3 (95% confidence interval, 1.3 to 8.8, 6 exposed infants).

Other studies have found varying results as to whether there was an increased risk of overall, cardiovascular, or specific congenital malformations. A meta-analysis of epidemiological data over a 16-year period (1992 to 2008) on first trimester paroxetine use in pregnancy and congenital malformations included the above-noted studies in addition to others (n = 17 studies that included overall malformations and n = 14 studies that included cardiovascular malformations; n = 20 distinct studies). While subject to limitations, this meta-analysis suggested an increased occurrence of cardiovascular malformations (prevalence odds ratio [POR] 1.5; 95% confidence interval 1.2 to 1.9) and overall malformations (POR 1.2; 95% confidence interval 1.1 to 1.4) with paroxetine use during the first trimester. It was not possible in this meta-analysis to determine the extent to which the observed prevalence of cardiovascular malformations might have contributed to that of overall malformations, nor was it possible to determine whether any specific types of cardiovascular malformations might have contributed to the observed prevalence of all cardiovascular malformations.

If a patient becomes pregnant while taking paroxetine, she should be advised of the potential harm to the fetus. Unless the benefits of paroxetine to the mother justify continuing treatment, consideration should be given to either discontinuing paroxetine therapy or switching to another antidepressant (see PRECAUTIONS: Discontinuation of Treatment With PAXIL). For women who intend to become pregnant or are in their first trimester of pregnancy, paroxetine should only be initiated after consideration of the other available treatment options.

Animal Findings

Reproduction studies were performed at doses up to 50 mg/kg/day in rats and 6 mg/kg/day in rabbits administered during organogenesis. These doses are approximately 8 (rat) and 2 (rabbit) times the maximum recommended human dose (MRHD) on an mg/m^2 basis. These studies have revealed no evidence of teratogenic effects. However, in rats, there was an increase in pup deaths during the first 4 days of lactation when dosing occurred during the last trimester of gestation and continued throughout lactation. This effect occurred at a dose of 1 mg/kg/day or approximately one-sixth of the MRHD on an mg/m^2 basis. The no-effect dose for rat pup mortality was not determined. The cause of these deaths is not known.

Nonteratogenic Effects

Neonates exposed to PAXIL and other SSRIs or serotonin and norepinephrine reuptake inhibitors (SNRIs), late in the third trimester have developed complications requiring prolonged hospitalization, respiratory support, and tube feeding. Such complications can arise immediately upon delivery. Reported clinical findings have included respiratory distress, cyanosis, apnea, seizures, temperature instability, feeding difficulty, vomiting, hypoglycemia, hypotonia, hypertonia, hyperreflexia, tremor, jitteriness, irritability, and constant crying. These features are consistent with either a direct toxic effect of SSRIs and SNRIs or, possibly, a drug discontinuation syndrome. It should be noted that, in some cases, the clinical picture is consistent with serotonin syndrome (see WARNINGS: Serotonin Syndrome or Neuroleptic Malignant Syndrome (NMS)-like Reactions).

Infants exposed to SSRIs in late pregnancy may have an increased risk for persistent pulmonary hypertension of the newborn (PPHN). PPHN occurs in 1 – 2 per 1,000 live births in the general population and is associated with substantial neonatal morbidity and mortality. In a retrospective case-control study of 377 women whose infants were born with PPHN and 836 women whose infants were born healthy, the risk for developing PPHN was approximately six-fold higher for infants exposed to SSRIs after the 20th week of gestation compared to infants who had not been exposed to antidepressants during pregnancy. There is currently no corroborative evidence regarding the risk for PPHN following exposure to SSRIs in pregnancy; this is the first study that has investigated the potential risk. The study did not include enough cases with exposure to individual SSRIs to determine if all SSRIs posed similar levels of PPHN risk.

There have also been postmarketing reports of premature births in pregnant women exposed to paroxetine or other SSRIs.

When treating a pregnant woman with paroxetine during the third trimester, the physician should carefully consider both the potential risks and benefits of treatment (see DOSAGE AND ADMINISTRATION). Physicians should note that in a prospective longitudinal study of 201 women with a history of major depression who were euthymic at the beginning of pregnancy, women who discontinued antidepressant medication during pregnancy were more likely to experience a relapse of major depression than women who continued antidepressant medication.

PRECAUTIONS

General

Activation of Mania/Hypomania

During premarketing testing, hypomania or mania occurred in approximately 1.0% of unipolar patients treated with PAXIL compared to 1.1% of active-control and 0.3% of placebo-treated unipolar patients. In a subset of patients classified as bipolar, the rate of manic episodes was 2.2% for PAXIL and 11.6% for the combined active-control groups. As with all drugs effective in the treatment of major depressive disorder, PAXIL should be used cautiously in patients with a history of mania.

Seizures

During premarketing testing, seizures occurred in 0.1% of patients treated with PAXIL, a rate similar to that associated with other drugs effective in the treatment of major depressive disorder. PAXIL should be used cautiously in patients with a history of seizures. It should be discontinued in any patient who develops seizures.

Discontinuation of Treatment With PAXIL

Recent clinical trials supporting the various approved indications for PAXIL employed a taper-phase regimen, rather than an abrupt discontinuation of treatment. The taper-phase regimen used in GAD and PTSD clinical trials involved an incremental decrease in the daily dose by 10 mg/day at weekly intervals. When a daily dose of 20 mg/day was reached, patients were continued on this dose for 1 week before treatment was stopped.

With this regimen in those studies, the following adverse events were reported at an incidence of 2% or greater for PAXIL and were at least twice that reported for placebo: Abnormal dreams, paresthesia, and dizziness. In the majority of patients, these events were mild to moderate and were self-limiting and did not require medical intervention.

During marketing of PAXIL and other SSRIs and SNRIs, there have been spontaneous reports of adverse events occurring upon the discontinuation of these drugs (particularly when abrupt), including the following: Dysphoric mood, irritability, agitation, dizziness, sensory disturbances (e.g., paresthesias such as electric shock sensations and tinnitus), anxiety, confusion, headache, lethargy, emotional lability, insomnia, and hypomania. While these events are generally self-limiting, there have been reports of serious discontinuation symptoms.

Patients should be monitored for these symptoms when discontinuing treatment with PAXIL. A gradual reduction in the dose rather than abrupt cessation is recommended whenever possible. If intolerable symptoms occur following a decrease in the dose or upon discontinuation of treatment, then resuming the previously prescribed dose may be considered. Subsequently, the physician may continue decreasing the dose but at a more gradual rate (see DOSAGE AND ADMINISTRATION).

See also PRECAUTIONS: Pediatric Use, for adverse events reported upon discontinuation of treatment with PAXIL in pediatric patients.

Tamoxifen

Some studies have shown that the efficacy of tamoxifen, as measured by the risk of breast cancer relapse/mortality, may be reduced when co-prescribed with paroxetine as a result of paroxetine’s irreversible inhibition of CYP2D6 (see Drug Interactions). However, other studies have failed to demonstrate such a risk. It is uncertain whether the coadministration of paroxetine and tamoxifen has a significant adverse effect on the efficacy of tamoxifen. One study suggests that the risk may increase with longer duration of coadministration. When tamoxifen is used for the treatment or prevention of breast cancer, prescribers should consider using an alternative antidepressant with little or no CYP2D6 inhibition.

Akathisia

The use of paroxetine or other SSRIs has been associated with the development of akathisia, which is characterized by an inner sense of restlessness and psychomotor agitation such as an inability to sit or stand still usually associated with subjective distress. This is most likely to occur within the first few weeks of treatment.

Hyponatremia

Hyponatremia may occur as a result of treatment with SSRIs and SNRIs, including PAXIL. In many cases, this hyponatremia appears to be the result of the syndrome of inappropriate antidiuretic hormone secretion (SIADH). Cases with serum sodium lower than 110 mmol/L have been reported. Elderly patients may be at greater risk of developing hyponatremia with SSRIs and SNRIs. Also, patients taking diuretics or who are otherwise volume depleted may be at greater risk (see PRECAUTIONS: Geriatric Use). Discontinuation of PAXIL should be considered in patients with symptomatic hyponatremia and appropriate medical intervention should be instituted.

Signs and symptoms of hyponatremia include headache, difficulty concentrating, memory impairment, confusion, weakness, and unsteadiness, which may lead to falls. Signs and symptoms associated with more severe and/or acute cases have included hallucination, syncope, seizure, coma, respiratory arrest, and death.

Abnormal Bleeding

SSRIs and SNRIs, including paroxetine, may increase the risk of bleeding events. Concomitant use of aspirin, nonsteroidal anti-inflammatory drugs, warfarin, and other anticoagulants may add to this risk. Case reports and epidemiological studies (case-control and cohort design) have demonstrated an association between use of drugs that interfere with serotonin reuptake and the occurrence of gastrointestinal bleeding. Bleeding events related to SSRIs and SNRIs use have ranged from ecchymoses, hematomas, epistaxis, and petechiae to life-threatening hemorrhages. Patients should be cautioned about the risk of bleeding associated with the concomitant use of paroxetine and NSAIDs, aspirin, or other drugs that affect coagulation.

Bone Fracture: Epidemiological studies on bone fracture risk following exposure to some antidepressants, including SSRIs, have reported an association between antidepressant treatment and fractures. There are multiple possible causes for this observation and it is unknown to what extent fracture risk is directly attributable to SSRI treatment. The possibility of a pathological fracture, that is, a fracture produced by minimal trauma in a patient with decreased bone mineral density, should be considered in patients treated with paroxetine who present with unexplained bone pain, point tenderness, swelling, or bruising.

Use in Patients With Concomitant Illness

Clinical experience with PAXIL in patients with certain concomitant systemic illness is limited. Caution is advisable in using PAXIL in patients with diseases or conditions that could affect metabolism or hemodynamic responses.

As with other SSRIs, mydriasis has been infrequently reported in premarketing studies with PAXIL. A few cases of acute angle closure glaucoma associated with paroxetine therapy have been reported in the literature. As mydriasis can cause acute angle closure in patients with narrow angle glaucoma, caution should be used when PAXIL is prescribed for patients with narrow angle glaucoma.

PAXIL has not been evaluated or used to any appreciable extent in patients with a recent history of myocardial infarction or unstable heart disease. Patients with these diagnoses were excluded from clinical studies during the product’s premarket testing. Evaluation of electrocardiograms of 682 patients who received PAXIL in double-blind, placebo-controlled trials, however, did not indicate that PAXIL is associated with the development of significant ECG abnormalities. Similarly, PAXIL does not cause any clinically important changes in heart rate or blood pressure.

Increased plasma concentrations of paroxetine occur in patients with severe renal impairment (creatinine clearance <30 mL/min.) or severe hepatic impairment. A lower starting dose should be used in such patients (see DOSAGE AND ADMINISTRATION).

Information for Patients

PAXIL should not be chewed or crushed, and should be swallowed whole.

Patients should be cautioned about the risk of serotonin syndrome with the concomitant use of PAXIL and triptans, tramadol, or other serotonergic agents.

Prescribers or other health professionals should inform patients, their families, and their caregivers about the benefits and risks associated with treatment with PAXIL and should counsel them in its appropriate use. A patient Medication Guide is available for PAXIL. The prescriber or health professional should instruct patients, their families, and their caregivers to read the Medication Guide and should assist them in understanding its contents. Patients should be given the opportunity to discuss the contents of the Medication Guide and to obtain answers to any questions they may have. The complete text of the Medication Guide is reprinted at the end of this document.

Patients should be advised of the following issues and asked to alert their prescriber if these occur while taking PAXIL.

Clinical Worsening and Suicide Risk

Patients, their families, and their caregivers should be encouraged to be alert to the emergence of anxiety, agitation, panic attacks, insomnia, irritability, hostility, aggressiveness, impulsivity, akathisia (psychomotor restlessness), hypomania, mania, other unusual changes in behavior, worsening of depression, and suicidal ideation, especially early during antidepressant treatment and when the dose is adjusted up or down. Families and caregivers of patients should be advised to look for the emergence of such symptoms on a day-to-day basis, since changes may be abrupt. Such symptoms should be reported to the patient’s prescriber or health professional, especially if they are severe, abrupt in onset, or were not part of the patient’s presenting symptoms. Symptoms such as these may be associated with an increased risk for suicidal thinking and behavior and indicate a need for very close monitoring and possibly changes in the medication.

Drugs That Interfere With Hemostasis (e.g., NSAIDs, Aspirin, and Warfarin)

Patients should be cautioned about the concomitant use of paroxetine and NSAIDs, aspirin, warfarin, or other drugs that affect coagulation since combined use of psychotropic drugs that interfere with serotonin reuptake and these agents has been associated with an increased risk of bleeding.

Interference With Cognitive and Motor Performance

Any psychoactive drug may impair judgment, thinking, or motor skills. Although in controlled studies PAXIL has not been shown to impair psychomotor performance, patients should be cautioned about operating hazardous machinery, including automobiles, until they are reasonably certain that therapy with PAXIL does not affect their ability to engage in such activities.

Completing Course of Therapy

While patients may notice improvement with treatment with PAXIL in 1 to 4 weeks, they should be advised to continue therapy as directed.

Concomitant Medication

Patients should be advised to inform their physician if they are taking, or plan to take, any prescription or over-the-counter drugs, since there is a potential for interactions.

Alcohol

Although PAXIL has not been shown to increase the impairment of mental and motor skills caused by alcohol, patients should be advised to avoid alcohol while taking PAXIL.

Pregnancy

Patients should be advised to notify their physician if they become pregnant or intend to become pregnant during therapy (see WARNINGS: Usage in Pregnancy: Teratogenic Effects and Nonteratogenic Effects).

Nursing

Patients should be advised to notify their physician if they are breastfeeding an infant (see PRECAUTIONS: Nursing Mothers).

Laboratory Tests

There are no specific laboratory tests recommended.

Drug Interactions

Tryptophan

As with other serotonin reuptake inhibitors, an interaction between paroxetine and tryptophan may occur when they are coadministered. Adverse experiences, consisting primarily of headache, nausea, sweating, and dizziness, have been reported when tryptophan was administered to patients taking PAXIL. Consequently, concomitant use of PAXIL with tryptophan is not recommended (see WARNINGS: Serotonin Syndrome or Neuroleptic Malignant Syndrome (NMS)-like Reactions).

Monoamine Oxidase Inhibitors

See CONTRAINDICATIONS and WARNINGS.

Pimozide

In a controlled study of healthy volunteers, after PAXIL was titrated to 60 mg daily, co-administration of a single dose of 2 mg pimozide was associated with mean increases in pimozide AUC of 151% and Cmax of 62%, compared to pimozide administered alone. The increase in pimozide AUC and Cmax is due to the CYP2D6 inhibitory properties of paroxetine. Due to the narrow therapeutic index of pimozide and its known ability to prolong the QT interval, concomitant use of pimozide and PAXIL is contraindicated (see CONTRAINDICATIONS).

Serotonergic Drugs

Based on the mechanism of action of SNRIs and SSRIs, including paroxetine hydrochloride, and the potential for serotonin syndrome, caution is advised when PAXIL is coadministered with other drugs that may affect the serotonergic neurotransmitter systems, such as triptans, lithium, fentanyl, tramadol, or St. John's Wort (see WARNINGS: Serotonin Syndrome or Neuroleptic Malignant Syndrome (NMS)-like Reactions). The concomitant use of PAXIL with MAOIs (including linezolid and methylene blue) is contraindicated (see CONTRAINDICATIONS). The concomitant use of PAXIL with other SSRIs, SNRIs or tryptophan is not recommended (see PRECAUTIONS: Drug Interactions: Tryptophan).

Thioridazine

See CONTRAINDICATIONS and WARNINGS.

Warfarin

Preliminary data suggest that there may be a pharmacodynamic interaction (that causes an increased bleeding diathesis in the face of unaltered prothrombin time) between paroxetine and warfarin. Since there is little clinical experience, the concomitant administration of PAXIL and warfarin should be undertaken with caution (see PRECAUTIONS: Drugs That Interfere With Hemostasis).

Triptans

There have been rare postmarketing reports of serotonin syndrome with the use of an SSRI and a triptan. If concomitant use of PAXIL with a triptan is clinically warranted, careful observation of the patient is advised, particularly during treatment initiation and dose increases (see WARNINGS: Serotonin Syndrome or Neuroleptic Malignant Syndrome (NMS)-like Reactions).

Drugs Affecting Hepatic Metabolism

The metabolism and pharmacokinetics of paroxetine may be affected by the induction or inhibition of drug-metabolizing enzymes.

Cimetidine

Cimetidine inhibits many cytochrome P450 (oxidative) enzymes. In a study where PAXIL (30 mg once daily) was dosed orally for 4 weeks, steady-state plasma concentrations of paroxetine were increased by approximately 50% during coadministration with oral cimetidine (300 mg three times daily) for the final week. Therefore, when these drugs are administered concurrently, dosage adjustment of PAXIL after the 20-mg starting dose should be guided by clinical effect. The effect of paroxetine on cimetidine’s pharmacokinetics was not studied.

Phenobarbital

Phenobarbital induces many cytochrome P450 (oxidative) enzymes. When a single oral 30-mg dose of PAXIL was administered at phenobarbital steady state (100 mg once daily for 14 days), paroxetine AUC and T½ were reduced (by an average of 25% and 38%, respectively) compared to paroxetine administered alone. The effect of paroxetine on phenobarbital pharmacokinetics was not studied. Since PAXIL exhibits nonlinear pharmacokinetics, the results of this study may not address the case where the 2 drugs are both being chronically dosed. No initial dosage adjustment of PAXIL is considered necessary when coadministered with phenobarbital; any subsequent adjustment should be guided by clinical effect.

Phenytoin

When a single oral 30-mg dose of PAXIL was administered at phenytoin steady state (300 mg once daily for 14 days), paroxetine AUC and T½ were reduced (by an average of 50% and 35%, respectively) compared to PAXIL administered alone. In a separate study, when a single oral 300-mg dose of phenytoin was administered at paroxetine steady state (30 mg once daily for 14 days), phenytoin AUC was slightly reduced (12% on average) compared to phenytoin administered alone. Since both drugs exhibit nonlinear pharmacokinetics, the above studies may not address the case where the 2 drugs are both being chronically dosed. No initial dosage adjustments are considered necessary when these drugs are coadministered; any subsequent adjustments should be guided by clinical effect (see ADVERSE REACTIONS: Postmarketing Reports).

Drugs Metabolized by CYP2D6

Many drugs, including most drugs effective in the treatment of major depressive disorder (paroxetine, other SSRIs and many tricyclics), are metabolized by the cytochrome P450 isozyme CYP2D6. Like other agents that are metabolized by CYP2D6, paroxetine may significantly inhibit the activity of this isozyme. In most patients (>90%), this CYP2D6 isozyme is saturated early during dosing with PAXIL. In 1 study, daily dosing of PAXIL (20 mg once daily) under steady-state conditions increased single dose desipramine (100 mg) Cmax, AUC, and T½ by an average of approximately 2-, 5-, and 3-fold, respectively. Concomitant use of paroxetine with risperidone, a CYP2D6 substrate has also been evaluated. In 1 study, daily dosing of paroxetine 20 mg in patients stabilized on risperidone (4 to 8 mg/day) increased mean plasma concentrations of risperidone approximately 4-fold, decreased 9-hydroxyrisperidone concentrations approximately 10%, and increased concentrations of the active moiety (the sum of risperidone plus 9-hydroxyrisperidone) approximately 1.4-fold. The effect of paroxetine on the pharmacokinetics of atomoxetine has been evaluated when both drugs were at steady state. In healthy volunteers who were extensive metabolizers of CYP2D6, paroxetine 20 mg daily was given in combination with 20 mg atomoxetine every 12 hours. This resulted in increases in steady state atomoxetine AUC values that were 6- to 8-fold greater and in atomoxetine Cmax values that were 3- to 4-fold greater than when atomoxetine was given alone. Dosage adjustment of atomoxetine may be necessary and it is recommended that atomoxetine be initiated at a reduced dose when it is given with paroxetine.

Concomitant use of PAXIL with other drugs metabolized by cytochrome CYP2D6 has not been formally studied but may require lower doses than usually prescribed for either PAXIL or the other drug.

Therefore, coadministration of PAXIL with other drugs that are metabolized by this isozyme, including certain drugs effective in the treatment of major depressive disorder (e.g., nortriptyline, amitriptyline, imipramine, desipramine, and fluoxetine), phenothiazines, risperidone, and Type 1C antiarrhythmics (e.g., propafenone, flecainide, and encainide), or that inhibit this enzyme (e.g., quinidine), should be approached with caution.

However, due to the risk of serious ventricular arrhythmias and sudden death potentially associated with elevated plasma levels of thioridazine, paroxetine and thioridazine should not be coadministered (see CONTRAINDICATIONS and WARNINGS).

Tamoxifen is a pro-drug requiring metabolic activation by CYP2D6. Inhibition of CYP2D6 by paroxetine may lead to reduced plasma concentrations of an active metabolite (endoxifen) and hence reduced efficacy of tamoxifen (see PRECAUTIONS).

At steady state, when the CYP2D6 pathway is essentially saturated, paroxetine clearance is governed by alternative P450 isozymes that, unlike CYP2D6, show no evidence of saturation (see PRECAUTIONS: Tricyclic Antidepressants [TCAs]).

Drugs Metabolized by Cytochrome CYP3A4

An in vivo interaction study involving the coadministration under steady-state conditions of paroxetine and terfenadine, a substrate for cytochrome CYP3A4, revealed no effect of paroxetine on terfenadine pharmacokinetics. In addition, in vitro studies have shown ketoconazole, a potent inhibitor of CYP3A4 activity, to be at least 100 times more potent than paroxetine as an inhibitor of the metabolism of several substrates for this enzyme, including terfenadine, astemizole, cisapride, triazolam, and cyclosporine. Based on the assumption that the relationship between paroxetine’s in vitro Ki and its lack of effect on terfenadine’s in vivo clearance predicts its effect on other CYP3A4 substrates, paroxetine’s extent of inhibition of CYP3A4 activity is not likely to be of clinical significance.

Tricyclic Antidepressants (TCAs)

Caution is indicated in the coadministration of tricyclic antidepressants (TCAs) with PAXIL, because paroxetine may inhibit TCA metabolism. Plasma TCA concentrations may need to be monitored, and the dose of TCA may need to be reduced, if a TCA is coadministered with PAXIL (see PRECAUTIONS: Drugs Metabolized by Cytochrome CYP2D6).

Drugs Highly Bound to Plasma Protein

Because paroxetine is highly bound to plasma protein, administration of PAXIL to a patient taking another drug that is highly protein bound may cause increased free concentrations of the other drug, potentially resulting in adverse events. Conversely, adverse effects could result from displacement of paroxetine by other highly bound drugs.

Drugs That Interfere With Hemostasis (e.g., NSAIDs, Aspirin, and Warfarin)

Serotonin release by platelets plays an important role in hemostasis. Epidemiological studies of the case-control and cohort design that have demonstrated an association between use of psychotropic drugs that interfere with serotonin reuptake and the occurrence of upper gastrointestinal bleeding have also shown that concurrent use of an NSAID or aspirin may potentiate this risk of bleeding. Altered anticoagulant effects, including increased bleeding, have been reported when SSRIs or SNRIs are coadministered with warfarin. Patients receiving warfarin therapy should be carefully monitored when paroxetine is initiated or discontinued.

Alcohol

Although PAXIL does not increase the impairment of mental and motor skills caused by alcohol, patients should be advised to avoid alcohol while taking PAXIL.

Lithium

A multiple-dose study has shown that there is no pharmacokinetic interaction between PAXIL and lithium carbonate. However, due to the potential for serotonin syndrome, caution is advised when PAXIL is coadministered with lithium.

Digoxin

The steady-state pharmacokinetics of paroxetine was not altered when administered with digoxin at steady state. Mean digoxin AUC at steady state decreased by 15% in the presence of paroxetine. Since there is little clinical experience, the concurrent administration of paroxetine and digoxin should be undertaken with caution.

Diazepam

Under steady-state conditions, diazepam does not appear to affect paroxetine kinetics. The effects of paroxetine on diazepam were not evaluated.

Procyclidine

Daily oral dosing of PAXIL (30 mg once daily) increased steady-state AUC0-24, Cmax, and Cmin values of procyclidine (5 mg oral once daily) by 35%, 37%, and 67%, respectively, compared to procyclidine alone at steady state. If anticholinergic effects are seen, the dose of procyclidine should be reduced.

Beta-Blockers

In a study where propranolol (80 mg twice daily) was dosed orally for 18 days, the established steady-state plasma concentrations of propranolol were unaltered during coadministration with PAXIL (30 mg once daily) for the final 10 days. The effects of propranolol on paroxetine have not been evaluated (see ADVERSE REACTIONS: Postmarketing Reports).

Theophylline

Reports of elevated theophylline levels associated with treatment with PAXIL have been reported. While this interaction has not been formally studied, it is recommended that theophylline levels be monitored when these drugs are concurrently administered.

Fosamprenavir/Ritonavir

Co-administration of fosamprenavir/ritonavir with paroxetine significantly decreased plasma levels of paroxetine. Any dose adjustment should be guided by clinical effect (tolerability and efficacy).

Electroconvulsive Therapy (ECT)

There are no clinical studies of the combined use of ECT and PAXIL.

Carcinogenesis, Mutagenesis, Impairment of Fertility

Carcinogenesis

Two-year carcinogenicity studies were conducted in rodents given paroxetine in the diet at 1, 5, and 25 mg/kg/day (mice) and 1, 5, and 20 mg/kg/day (rats). These doses are up to 2.4 (mouse) and 3.9 (rat) times the MRHD for major depressive disorder, social anxiety disorder, GAD, and PTSD on a mg/m^2 basis. Because the MRHD for major depressive disorder is slightly less than that for OCD (50 mg versus 60 mg), the doses used in these carcinogenicity studies were only 2.0 (mouse) and 3.2 (rat) times the MRHD for OCD. There was a significantly greater number of male rats in the high-dose group with reticulum cell sarcomas (1/100, 0/50, 0/50, and 4/50 for control, low-, middle-, and high-dose groups, respectively) and a significantly increased linear trend across dose groups for the occurrence of lymphoreticular tumors in male rats. Female rats were not affected. Although there was a dose-related increase in the number of tumors in mice, there was no drug-related increase in the number of mice with tumors. The relevance of these findings to humans is unknown.

Mutagenesis

Paroxetine produced no genotoxic effects in a battery of 5 in vitro and 2 in vivo assays that included the following: Bacterial mutation assay, mouse lymphoma mutation assay, unscheduled DNA synthesis assay, and tests for cytogenetic aberrations in vivo in mouse bone marrow and in vitro in human lymphocytes and in a dominant lethal test in rats.

Impairment of Fertility

Some clinical studies have shown that SSRIs (including paroxetine) may affect sperm quality during SSRI treatment, which may affect fertility in some men.

A reduced pregnancy rate was found in reproduction studies in rats at a dose of paroxetine of 15 mg/kg/day, which is 2.9 times the MRHD for major depressive disorder, social anxiety disorder, GAD, and PTSD or 2.4 times the MRHD for OCD on a mg/m^2 basis. Irreversible lesions occurred in the reproductive tract of male rats after dosing in toxicity studies for 2 to 52 weeks. These lesions consisted of vacuolation of epididymal tubular epithelium at 50 mg/kg/day and atrophic changes in the seminiferous tubules of the testes with arrested spermatogenesis at 25 mg/kg/day (9.8 and 4.9 times the MRHD for major depressive disorder, social anxiety disorder, and GAD; 8.2 and 4.1 times the MRHD for OCD and PD on a mg/m^2 basis).

Pregnancy

Pregnancy Category D. See WARNINGS—Usage in Pregnancy: Teratogenic Effects and Nonteratogenic Effects.

Labor and Delivery

The effect of paroxetine on labor and delivery in humans is unknown.

Nursing Mothers

Like many other drugs, paroxetine is secreted in human milk, and caution should be exercised when PAXIL is administered to a nursing woman.

Pediatric Use

Safety and effectiveness in the pediatric population have not been established (see BOX WARNING and WARNINGS: Clinical Worsening and Suicide Risk). Three placebo-controlled trials in 752 pediatric patients with MDD have been conducted with PAXIL, and the data were not sufficient to support a claim for use in pediatric patients. Anyone considering the use of PAXIL in a child or adolescent must balance the potential risks with the clinical need. Decreased appetite and weight loss have been observed in association with the use of SSRIs. Consequently, regular monitoring of weight and growth should be performed in children and adolescents treated with an SSRI such as PAXIL.

In placebo-controlled clinical trials conducted with pediatric patients, the following adverse events were reported in at least 2% of pediatric patients treated with PAXIL and occurred at a rate at least twice that for pediatric patients receiving placebo: emotional lability (including self-harm, suicidal thoughts, attempted suicide, crying, and mood fluctuations), hostility, decreased appetite, tremor, sweating, hyperkinesia, and agitation.

Events reported upon discontinuation of treatment with PAXIL in the pediatric clinical trials that included a taper phase regimen, which occurred in at least 2% of patients who received PAXIL and which occurred at a rate at least twice that of placebo, were: emotional lability (including suicidal ideation, suicide attempt, mood changes, and tearfulness), nervousness, dizziness, nausea, and abdominal pain (see DOSAGE AND ADMINISTRATION: Discontinuation of Treatment With PAXIL).

Geriatric Use

SSRIs and SNRIs, including PAXIL, have been associated with cases of clinically significant hyponatremia in elderly patients, who may be at greater risk for this adverse event (see PRECAUTIONS: Hyponatremia).

In worldwide premarketing clinical trials with PAXIL, 17% of patients treated with PAXIL (approximately 700) were 65 years of age or older. Pharmacokinetic studies revealed a decreased clearance in the elderly, and a lower starting dose is recommended; there were, however, no overall differences in the adverse event profile between elderly and younger patients, and effectiveness was similar in younger and older patients (see CLINICAL PHARMACOLOGY and DOSAGE AND ADMINISTRATION).

ADVERSE REACTIONS

Associated With Discontinuation of Treatment

Twenty percent (1,199/6,145) of patients treated with PAXIL in worldwide clinical trials in major depressive disorder and 16.1% (84/522), 11.8% (64/542), 9.4% (44/469), 10.7% (79/735), and 11.7% (79/676) of patients treated with PAXIL in worldwide trials in social anxiety disorder, OCD, panic disorder, GAD, and PTSD, respectively, discontinued treatment due to an adverse event. The most common events (≥1%) associated with discontinuation and considered to be drug related (i.e., those events associated with dropout at a rate approximately twice or greater for PAXIL compared to placebo) included the following:

 | Major Depressive Disorder |  | OCD |  | Panic Disorder |  | Social Anxiety Disorder |  | Generalized Anxiety Disorder |  | PTSD
 | PAXIL | Placebo | PAXIL | Placebo | PAXIL | Placebo | PAXIL | Placebo | PAXIL | Placebo | PAXIL | Placebo
CNS
Somnolence | 2.3% | 0.7% | — |  | 1.9% | 0.3% | 3.4% | 0.3% | 2.0% | 0.2% | 2.8% | 0.6%
Insomnia | — | — | 1.7% | 0% | 1.3% | 0.3% | 3.1% | 0% |  |  | — | —
Agitation | 1.1% | 0.5% | — |  |  |  |  |  |  |  | — | —
Tremor | 1.1% | 0.3% | — |  |  |  | 1.7% | 0% |  |  | 1.0% | 0.2%
Anxiety | — | — | — |  |  |  | 1.1% | 0% |  |  | — | —
Dizziness | — | — | 1.5% | 0% |  |  | 1.9% | 0% | 1.0% | 0.2% | — | —
Gastroin-testinal
Constipation | — |  | 1.1% | 0% |  |  |  |  |  |  | — | —
Nausea | 3.2% | 1.1% | 1.9% | 0% | 3.2% | 1.2% | 4.0% | 0.3% | 2.0% | 0.2% | 2.2% | 0.6%
Diarrhea | 1.0% | 0.3% | —
Dry mouth | 1.0% | 0.3% | — |  |  |  |  |  |  |  | — | —
Vomiting | 1.0% | 0.3% | — |  |  |  | 1.0% | 0% |  |  | — | —
Flatulence |  |  |  |  |  |  | 1.0% | 0.3% |  |  | — | —
Other
Asthenia | 1.6% | 0.4% | 1.9% | 0.4% |  |  | 2.5% | 0.6% | 1.8% | 0.2% | 1.6% | 0.2%
Abnormal; Ejaculationa | 1.6% | 0% | 2.1% | 0% |  |  | 4.9% | 0.6% | 2.5% | 0.5% | — | —
Sweating | 1.0% | 0.3% | — |  |  |  | 1.1% | 0% | 1.1% | 0.2% | — | —
Impotencea | — |  | 1.5% | 0% |  |  |  |  |  |  | — | —
Libido; Decreased |  |  |  |  |  |  | 1.0% | 0% |  |  | — | —

Where numbers are not provided the incidence of the adverse events in patients treated with PAXIL was not >1% or was not greater than or equal to 2 times the incidence of placebo.

a Incidence corrected for gender.

Commonly Observed Adverse Events

Major Depressive Disorder

The most commonly observed adverse events associated with the use of paroxetine (incidence of 5% or greater and incidence for PAXIL at least twice that for placebo, derived from Table 2) were: Asthenia, sweating, nausea, decreased appetite, somnolence, dizziness, insomnia, tremor, nervousness, ejaculatory disturbance, and other male genital disorders.

Obsessive Compulsive Disorder

The most commonly observed adverse events associated with the use of paroxetine (incidence of 5% or greater and incidence for PAXIL at least twice that of placebo, derived from Table 3) were: Nausea, dry mouth, decreased appetite, constipation, dizziness, somnolence, tremor, sweating, impotence, and abnormal ejaculation.

Panic Disorder

The most commonly observed adverse events associated with the use of paroxetine (incidence of 5% or greater and incidence for PAXIL at least twice that for placebo, derived from Table 3) were: Asthenia, sweating, decreased appetite, libido decreased, tremor, abnormal ejaculation, female genital disorders, and impotence.

Social Anxiety Disorder

The most commonly observed adverse events associated with the use of paroxetine (incidence of 5% or greater and incidence for PAXIL at least twice that for placebo, derived from Table 3) were: Sweating, nausea, dry mouth, constipation, decreased appetite, somnolence, tremor, libido decreased, yawn, abnormal ejaculation, female genital disorders, and impotence.

Generalized Anxiety Disorder

The most commonly observed adverse events associated with the use of paroxetine (incidence of 5% or greater and incidence for PAXIL at least twice that for placebo, derived from Table 4) were: Asthenia, infection, constipation, decreased appetite, dry mouth, nausea, libido decreased, somnolence, tremor, sweating, and abnormal ejaculation.

Posttraumatic Stress Disorder

The most commonly observed adverse events associated with the use of paroxetine (incidence of 5% or greater and incidence for PAXIL at least twice that for placebo, derived from Table 4) were: Asthenia, sweating, nausea, dry mouth, diarrhea, decreased appetite, somnolence, libido decreased, abnormal ejaculation, female genital disorders, and impotence.

Incidence in Controlled Clinical Trials

The prescriber should be aware that the figures in the tables following cannot be used to predict the incidence of side effects in the course of usual medical practice where patient characteristics and other factors differ from those that prevailed in the clinical trials. Similarly, the cited frequencies cannot be compared with figures obtained from other clinical investigations involving different treatments, uses, and investigators. The cited figures, however, do provide the prescribing physician with some basis for estimating the relative contribution of drug and nondrug factors to the side effect incidence rate in the populations studied.

Major Depressive Disorder

Table 2 enumerates adverse events that occurred at an incidence of 1% or more among paroxetine-treated patients who participated in short-term (6-week) placebo-controlled trials in which patients were dosed in a range of 20 mg to 50 mg/day. Reported adverse events were classified using a standard COSTART-based Dictionary terminology.

Table 2. Treatment-Emergent Adverse Experience Incidence in Placebo-Controlled Clinical Trials for Major Depressive Disordera
Body System | Preferred Term | PAXIL; (n = 421) | Placebo; (n = 421)
Body as a Whole | Headache | 18% | 17%
 | Asthenia | 15% | 6%
Cardiovascular | Palpitation | 3% | 1%
 | Vasodilation | 3% | 1%
Dermatologic | Sweating | 11% | 2%
 | Rash | 2% | 1%
Gastrointestinal | Nausea | 26% | 9%
 | Dry Mouth | 18% | 12%
 | Constipation | 14% | 9%
 | Diarrhea | 12% | 8%
 | Decreased Appetite | 6% | 2%
 | Flatulence | 4% | 2%
 | Oropharynx Disorderb | 2% | 0%
 | Dyspepsia | 2% | 1%
Musculoskeletal | Myopathy | 2% | 1%
 | Myalgia | 2% | 1%
 | Myasthenia | 1% | 0%
Nervous System | Somnolence | 23% | 9%
 | Dizziness | 13% | 6%
 | Insomnia | 13% | 6%
 | Tremor | 8% | 2%
 | Nervousness | 5% | 3%
 | Anxiety | 5% | 3%
 | Paresthesia | 4% | 2%
 | Libido Decreased | 3% | 0%
 | Drugged Feeling | 2% | 1%
 | Confusion | 1% | 0%
Respiration | Yawn | 4% | 0%
Special Senses | Blurred Vision | 4% | 1%
 | Taste Perversion | 2% | 0%
Urogenital System | Ejaculatory Disturbance c,d | 13% | 0%
 | Other Male Genital Disordersc,e | 10% | 0%
 | Urinary Frequency | 3% | 1%
 | Urination Disorderf | 3% | 0%
 | Female Genital Disordersc,g | 2% | 0%

a Events reported by at least 1% of patients treated with PAXIL are included, except the following events which had an incidence on placebo ≥ PAXIL: Abdominal pain, agitation, back pain, chest pain, CNS stimulation, fever, increased appetite, myoclonus, pharyngitis, postural hypotension, respiratory disorder (includes mostly “cold symptoms” or “URI”), trauma, and vomiting.

b Includes mostly “lump in throat” and “tightness in throat.”

c Percentage corrected for gender.

d Mostly “ejaculatory delay.”

e Includes “anorgasmia,” “erectile difficulties,” “delayed ejaculation/orgasm,” and “sexual dysfunction,” and “impotence.”

f Includes mostly “difficulty with micturition” and “urinary hesitancy.”

g Includes mostly “anorgasmia” and “difficulty reaching climax/orgasm.”

Obsessive Compulsive Disorder, Panic Disorder, and Social Anxiety Disorder

Table 3 enumerates adverse events that occurred at a frequency of 2% or more among OCD patients on PAXIL who participated in placebo-controlled trials of 12-weeks duration in which patients were dosed in a range of 20 mg to 60 mg/day or among patients with panic disorder on PAXIL who participated in placebo-controlled trials of 10- to 12-weeks duration in which patients were dosed in a range of 10 mg to 60 mg/day or among patients with social anxiety disorder on PAXIL who participated in placebo-controlled trials of 12-weeks duration in which patients were dosed in a range of 20 mg to 50 mg/day.

Table 3. Treatment-Emergent Adverse Experience Incidence in Placebo-Controlled Clinical Trials for Obsessive Compulsive Disorder, Panic Disorder, and Social Anxiety Disordera
Body System | Preferred Term | Obsessive; Compulsive; Disorder |  | Panic; Disorder |  | Social Anxiety; Disorder
Body System | Preferred Term | PAXIL; (n = 542) | Placebo; (n = 265) | PAXIL; (n = 469) | Placebo; (n = 324) | PAXIL; (n = 425) | Placebo; (n = 339)
Body as a Whole | Asthenia | 22% | 14% | 14% | 5% | 22% | 14%
 | Abdominal Pain | — | — | 4% | 3% | — | —
 | Chest Pain | 3% | 2% | — | — | — | —
 | Back Pain | — | — | 3% | 2% | — | —
 | Chills | 2% | 1% | 2% | 1% | — | —
 | Trauma | — | — | — | — | 3% | 1%
Cardiovascular | Vasodilation | 4% | 1% | — | — | — | —
 | Palpitation | 2% | 0% | — | — | — | —
Dermatologic | Sweating | 9% | 3% | 14% | 6% | 9% | 2%
 | Rash | 3% | 2% | — | — | — | —
Gastrointestinal | Nausea | 23% | 10% | 23% | 17% | 25% | 7%
 | Dry Mouth | 18% | 9% | 18% | 11% | 9% | 3%
 | Constipation | 16% | 6% | 8% | 5% | 5% | 2%
 | Diarrhea | 10% | 10% | 12% | 7% | 9% | 6%
 | Decreased; Appetite | 9% | 3% | 7% | 3% | 8% | 2%
 | Dyspepsia | — | — | — | — | 4% | 2%
 | Flatulence | — | — | — | — | 4% | 2%
 | Increased; Appetite | 4% | 3% | 2% | 1% | — | —
 | Vomiting | — | — | — | — | 2% | 1%
Musculoskeletal | Myalgia | — | — | — | — | 4% | 3%
Nervous System | Insomnia | 24% | 13% | 18% | 10% | 21% | 16%
 | Somnolence | 24% | 7% | 19% | 11% | 22% | 5%
 | Dizziness | 12% | 6% | 14% | 10% | 11% | 7%
 | Tremor | 11% | 1% | 9% | 1% | 9% | 1%
 | Nervousness | 9% | 8% | — | — | 8% | 7%
 | Libido Decreased | 7% | 4% | 9% | 1% | 12% | 1%
 | Agitation | — | — | 5% | 4% | 3% | 1%
 | Anxiety | — | — | 5% | 4% | 5% | 4%
 | Abnormal; Dreams | 4% | 1% | — | — | — | —
 | Concentration; Impaired | 3% | 2% | — | — | 4% | 1%
 | Depersonalization | 3% | 0% | — | — | — | —
 | Myoclonus | 3% | 0% | 3% | 2% | 2% | 1%
 | Amnesia | 2% | 1% | — | — | — | —
Respiratory System | Rhinitis | — | — | 3% | 0% | — | —
 | Pharyngitis | — | — | — | — | 4% | 2%
 | Yawn | — | — | — | — | 5% | 1%
Special Senses | Abnormal Vision | 4% | 2% | — | — | 4% | 1%
 | Taste Perversion | 2% | 0% | — | — | — | —
Urogenital System | Abnormal; Ejaculationb | 23% | 1% | 21% | 1% | 28% | 1%
 | Dysmenorrhea | — | — | — | — | 5% | 4%
 | Female Genital; Disorderb | 3% | 0% | 9% | 1% | 9% | 1%
 | Impotenceb | 8% | 1% | 5% | 0% | 5% | 1%
 | Urinary; Frequency | 3% | 1% | 2% | 0% | — | —
 | Urination; Impaired | 3% | 0% | — | — | — | —
 | Urinary Tract; Infection | 2% | 1% | 2% | 1% | — | —

a Events reported by at least 2% of OCD, panic disorder, and social anxiety disorder in patients treated with PAXIL are included, except the following events which had an incidence on placebo ≥PAXIL: [OCD]: Abdominal pain, agitation, anxiety, back pain, cough increased, depression, headache, hyperkinesia, infection, paresthesia, pharyngitis, respiratory disorder, rhinitis, and sinusitis. [panic disorder]: Abnormal dreams, abnormal vision, chest pain, cough increased, depersonalization, depression, dysmenorrhea, dyspepsia, flu syndrome, headache, infection, myalgia, nervousness, palpitation, paresthesia, pharyngitis, rash, respiratory disorder, sinusitis, taste perversion, trauma, urination impaired, and vasodilation. [social anxiety disorder]: Abdominal pain, depression, headache, infection, respiratory disorder, and sinusitis.

b Percentage corrected for gender.

Generalized Anxiety Disorder and Posttraumatic Stress Disorder

Table 4 enumerates adverse events that occurred at a frequency of 2% or more among GAD patients on PAXIL who participated in placebo-controlled trials of 8-weeks duration in which patients were dosed in a range of 10 mg/day to 50 mg/day or among PTSD patients on PAXIL who participated in placebo-controlled trials of 12-weeks duration in which patients were dosed in a range of 20 mg/day to 50 mg/day.

Table 4. Treatment-Emergent Adverse Experience Incidence in Placebo-Controlled Clinical Trials for Generalized Anxiety Disorder and Posttraumatic Stress Disordera
Body System | Preferred Term | Generalized Anxiety Disorder |  | Posttraumatic Stress Disorder
Body System | Preferred Term | PAXIL; (n = 735) | Placebo; (n = 529) | PAXIL; (n = 676) | Placebo; (n = 504)
Body as a Whole | Asthenia | 14% | 6% | 12% | 4%
Body as a Whole | Headache | 17% | 14% | — | —
Body as a Whole | Infection | 6% | 3% | 5% | 4%
Body as a Whole | Abdominal Pain |  |  | 4% | 3%
Body as a Whole | Trauma |  |  | 6% | 5%
Cardiovascular | Vasodilation | 3% | 1% | 2% | 1%
Dermatologic | Sweating | 6% | 2% | 5% | 1%
Gastrointestinal | Nausea | 20% | 5% | 19% | 8%
Gastrointestinal | Dry Mouth | 11% | 5% | 10% | 5%
Gastrointestinal | Constipation | 10% | 2% | 5% | 3%
Gastrointestinal | Diarrhea | 9% | 7% | 11% | 5%
Gastrointestinal | Decreased Appetite | 5% | 1% | 6% | 3%
Gastrointestinal | Vomiting | 3% | 2% | 3% | 2%
Gastrointestinal | Dyspepsia | — | — | 5% | 3%
Nervous System | Insomnia | 11% | 8% | 12% | 11%
Nervous System | Somnolence | 15% | 5% | 16% | 5%
Nervous System | Dizziness | 6% | 5% | 6% | 5%
Nervous System | Tremor | 5% | 1% | 4% | 1%
Nervous System | Nervousness | 4% | 3% | — | —
Nervous System | Libido Decreased | 9% | 2% | 5% | 2%
Nervous System | Abnormal Dreams |  |  | 3% | 2%
Respiratory System | Respiratory Disorder | 7% | 5% | — | —
Respiratory System | Sinusitis | 4% | 3% | — | —
Respiratory System | Yawn | 4% | — | 2% | <1%
Special Senses | Abnormal Vision | 2% | 1% | 3% | 1%
Urogenital System | Abnormal Ejaculationb | 25% | 2% | 13% | 2%
Urogenital System | Female Genital Disorderb | 4% | 1% | 5% | 1%
Urogenital System | Impotenceb | 4% | 3% | 9% | 1%

a. Events reported by at least 2% of GAD and PTSD in patients treated with PAXIL are included, except the following events which had an incidence on placebo ≥PAXIL [GAD]: Abdominal pain, back pain, trauma, dyspepsia, myalgia, and pharyngitis. [PTSD]: Back pain, headache, anxiety, depression, nervousness, respiratory disorder, pharyngitis, and sinusitis.

b. Percentage corrected for gender.

Dose Dependency of Adverse Events

A comparison of adverse event rates in a fixed-dose study comparing 10, 20, 30, and 40 mg/day of PAXIL with placebo in the treatment of major depressive disorder revealed a clear dose dependency for some of the more common adverse events associated with use of PAXIL, as shown in Table 5:

Table 5. Treatment-Emergent Adverse Experience Incidence in a Dose-Comparison Trial in the Treatment of Major Depressive Disordera
Body System/Preferred Term | Placebo | PAXIL
Body System/Preferred Term | n = 51 | 10 mg; n = 102 | 20 mg; n = 104 | 30 mg; n = 101 | 40 mg; n = 102
Body as a Whole
Asthenia | 0.0% | 2.9% | 10.6% | 13.9% | 12.7%
Dermatology
Sweating | 2.0% | 1.0% | 6.7% | 8.9% | 11.8%
Gastrointestinal
Constipation | 5.9% | 4.9% | 7.7% | 9.9% | 12.7%
Decreased Appetite | 2.0% | 2.0% | 5.8% | 4.0% | 4.9%
Diarrhea | 7.8% | 9.8% | 19.2% | 7.9% | 14.7%
Dry Mouth | 2.0% | 10.8% | 18.3% | 15.8% | 20.6%
Nausea | 13.7% | 14.7% | 26.9% | 34.7% | 36.3%
Nervous System
Anxiety | 0.0% | 2.0% | 5.8% | 5.9% | 5.9%
Dizziness | 3.9% | 6.9% | 6.7% | 8.9% | 12.7%
Nervousness | 0.0% | 5.9% | 5.8% | 4.0% | 2.9%
Paresthesia | 0.0% | 2.9% | 1.0% | 5.0% | 5.9%
Somnolence | 7.8% | 12.7% | 18.3% | 20.8% | 21.6%
Tremor | 0.0% | 0.0% | 7.7% | 7.9% | 14.7%
Special Senses
Blurred Vision | 2.0% | 2.9% | 2.9% | 2.0% | 7.8%
Urogenital System
Abnormal Ejaculation | 0.0% | 5.8% | 6.5% | 10.6% | 13.0%
Impotence | 0.0% | 1.9% | 4.3% | 6.4% | 1.9%
Male Genital Disorders | 0.0% | 3.8% | 8.7% | 6.4% | 3.7%

a Rule for including adverse events in table: Incidence at least 5% for 1 of paroxetine groups and ≥ twice the placebo incidence for at least 1 paroxetine group.

In a fixed-dose study comparing placebo and 20, 40, and 60 mg of PAXIL in the treatment of OCD, there was no clear relationship between adverse events and the dose of PAXIL to which patients were assigned. No new adverse events were observed in the group treated with 60 mg of PAXIL compared to any of the other treatment groups.

In a fixed-dose study comparing placebo and 10, 20, and 40 mg of PAXIL in the treatment of panic disorder, there was no clear relationship between adverse events and the dose of PAXIL to which patients were assigned, except for asthenia, dry mouth, anxiety, libido decreased, tremor, and abnormal ejaculation. In flexible-dose studies, no new adverse events were observed in patients receiving 60 mg of PAXIL compared to any of the other treatment groups.

In a fixed-dose study comparing placebo and 20, 40, and 60 mg of PAXIL in the treatment of social anxiety disorder, for most of the adverse events, there was no clear relationship between adverse events and the dose of PAXIL to which patients were assigned.

In a fixed-dose study comparing placebo and 20 and 40 mg of PAXIL in the treatment of generalized anxiety disorder, for most of the adverse events, there was no clear relationship between adverse events and the dose of PAXIL to which patients were assigned, except for the following adverse events: Asthenia, constipation, and abnormal ejaculation.

In a fixed-dose study comparing placebo and 20 and 40 mg of PAXIL in the treatment of posttraumatic stress disorder, for most of the adverse events, there was no clear relationship between adverse events and the dose of PAXIL to which patients were assigned, except for impotence and abnormal ejaculation.

Adaptation to Certain Adverse Events

Over a 4- to 6-week period, there was evidence of adaptation to some adverse events with continued therapy (e.g., nausea and dizziness), but less to other effects (e.g., dry mouth, somnolence, and asthenia).

Male and Female Sexual Dysfunction With SSRIs

Although changes in sexual desire, sexual performance, and sexual satisfaction often occur as manifestations of a psychiatric disorder, they may also be a consequence of pharmacologic treatment. In particular, some evidence suggests that selective serotonin reuptake inhibitors (SSRIs) can cause such untoward sexual experiences.

Reliable estimates of the incidence and severity of untoward experiences involving sexual desire, performance, and satisfaction are difficult to obtain, however, in part because patients and physicians may be reluctant to discuss them. Accordingly, estimates of the incidence of untoward sexual experience and performance cited in product labeling, are likely to underestimate their actual incidence.

In placebo-controlled clinical trials involving more than 3,200 patients, the ranges for the reported incidence of sexual side effects in males and females with major depressive disorder, OCD, panic disorder, social anxiety disorder, GAD, and PTSD are displayed in Table 6.

Table 6. Incidence of Sexual Adverse Events in Controlled Clinical Trials
 | PAXIL | Placebo
n (males) | 1446 | 1042
Decreased Libido | 6-15% | 0-5%
Ejaculatory Disturbance | 13-28% | 0-2%
Impotence | 2-9% | 0-3%
n (females) | 1822 | 1340
Decreased Libido | 0-9% | 0-2%
Orgasmic Disturbance | 2-9% | 0-1%

There are no adequate and well-controlled studies examining sexual dysfunction with paroxetine treatment.

Paroxetine treatment has been associated with several cases of priapism. In those cases with a known outcome, patients recovered without sequelae.

While it is difficult to know the precise risk of sexual dysfunction associated with the use of SSRIs, physicians should routinely inquire about such possible side effects.

Weight and Vital Sign Changes

Significant weight loss may be an undesirable result of treatment with PAXIL for some patients but, on average, patients in controlled trials had minimal (about 1 pound) weight loss versus smaller changes on placebo and active control. No significant changes in vital signs (systolic and diastolic blood pressure, pulse and temperature) were observed in patients treated with PAXIL in controlled clinical trials.

ECG Changes

In an analysis of ECGs obtained in 682 patients treated with PAXIL and 415 patients treated with placebo in controlled clinical trials, no clinically significant changes were seen in the ECGs of either group.

Liver Function Tests

In placebo-controlled clinical trials, patients treated with PAXIL exhibited abnormal values on liver function tests at no greater rate than that seen in placebo-treated patients. In particular, the PAXIL-versus-placebo comparisons for alkaline phosphatase, SGOT, SGPT, and bilirubin revealed no differences in the percentage of patients with marked abnormalities.

Hallucinations

In pooled clinical trials of immediate-release paroxetine hydrochloride, hallucinations were observed in 22 of 9089 patients receiving drug and 4 of 3187 patients receiving placebo.

Other Events Observed During the Premarketing Evaluation of PAXIL

During its premarketing assessment in major depressive disorder, multiple doses of PAXIL were administered to 6,145 patients in phase 2 and 3 studies. The conditions and duration of exposure to PAXIL varied greatly and included (in overlapping categories) open and double-blind studies, uncontrolled and controlled studies, inpatient and outpatient studies, and fixed-dose, and titration studies. During premarketing clinical trials in OCD, panic disorder, social anxiety disorder, generalized anxiety disorder, and posttraumatic stress disorder, 542, 469, 522, 735, and 676 patients, respectively, received multiple doses of PAXIL. Untoward events associated with this exposure were recorded by clinical investigators using terminology of their own choosing. Consequently, it is not possible to provide a meaningful estimate of the proportion of individuals experiencing adverse events without first grouping similar types of untoward events into a smaller number of standardized event categories.

In the tabulations that follow, reported adverse events were classified using a standard COSTART-based Dictionary terminology. The frequencies presented, therefore, represent the proportion of the 9,089 patients exposed to multiple doses of PAXIL who experienced an event of the type cited on at least 1 occasion while receiving PAXIL. All reported events are included except those already listed in Tables 2 to 5, those reported in terms so general as to be uninformative and those events where a drug cause was remote. It is important to emphasize that although the events reported occurred during treatment with paroxetine, they were not necessarily caused by it.

Events are further categorized by body system and listed in order of decreasing frequency according to the following definitions: Frequent adverse events are those occurring on 1 or more occasions in at least 1/100 patients (only those not already listed in the tabulated results from placebo-controlled trials appear in this listing); infrequent adverse events are those occurring in 1/100 to 1/1,000 patients; rare events are those occurring in fewer than 1/1,000 patients. Events of major clinical importance are also described in the PRECAUTIONS section.

Body as a Whole

Infrequent: Allergic reaction, chills, face edema, malaise, neck pain; rare: Adrenergic syndrome, cellulitis, moniliasis, neck rigidity, pelvic pain, peritonitis, sepsis, ulcer.

Cardiovascular System

Frequent: Hypertension, tachycardia; infrequent: Bradycardia, hematoma, hypotension, migraine, postural hypotension, syncope; rare: Angina pectoris, arrhythmia nodal, atrial fibrillation, bundle branch block, cerebral ischemia, cerebrovascular accident, congestive heart failure, heart block, low cardiac output, myocardial infarct, myocardial ischemia, pallor, phlebitis, pulmonary embolus, supraventricular extrasystoles, thrombophlebitis, thrombosis, varicose vein, vascular headache, ventricular extrasystoles.

Digestive System

Infrequent: Bruxism, colitis, dysphagia, eructation, gastritis, gastroenteritis, gingivitis, glossitis, increased salivation, liver function tests abnormal, rectal hemorrhage, ulcerative stomatitis; rare: Aphthous stomatitis, bloody diarrhea, bulimia, cardiospasm, cholelithiasis, duodenitis, enteritis, esophagitis, fecal impactions, fecal incontinence, gum hemorrhage, hematemesis, hepatitis, ileitis, ileus, intestinal obstruction, jaundice, melena, mouth ulceration, peptic ulcer, salivary gland enlargement, sialadenitis, stomach ulcer, stomatitis, tongue discoloration, tongue edema, tooth caries.

Endocrine System

Rare: Diabetes mellitus, goiter, hyperthyroidism, hypothyroidism, thyroiditis.

Hemic and Lymphatic Systems

Infrequent: Anemia, leukopenia, lymphadenopathy, purpura; rare: Abnormal erythrocytes, basophilia, bleeding time increased, eosinophilia, hypochromic anemia, iron deficiency anemia, leukocytosis, lymphedema, abnormal lymphocytes, lymphocytosis, microcytic anemia, monocytosis, normocytic anemia, thrombocythemia, thrombocytopenia.

Metabolic and Nutritional

Frequent: Weight gain; infrequent: Edema, peripheral edema, SGOT increased, SGPT increased, thirst, weight loss; rare: Alkaline phosphatase increased, bilirubinemia, BUN increased, creatinine phosphokinase increased, dehydration, gamma globulins increased, gout, hypercalcemia, hypercholesteremia, hyperglycemia, hyperkalemia, hyperphosphatemia, hypocalcemia, hypoglycemia, hypokalemia, hyponatremia, ketosis, lactic dehydrogenase increased, non-protein nitrogen (NPN) increased.

Musculoskeletal System

Frequent: Arthralgia; infrequent: Arthritis, arthrosis; rare: Bursitis, myositis, osteoporosis, generalized spasm, tenosynovitis, tetany.

Nervous System

Frequent: Emotional lability, vertigo; infrequent: Abnormal thinking, alcohol abuse, ataxia, dystonia, dyskinesia, euphoria, hallucinations, hostility, hypertonia, hypesthesia, hypokinesia, incoordination, lack of emotion, libido increased, manic reaction, neurosis, paralysis, paranoid reaction; rare: Abnormal gait, akinesia, antisocial reaction, aphasia, choreoathetosis, circumoral paresthesias, convulsion, delirium, delusions, diplopia, drug dependence, dysarthria, extrapyramidal syndrome, fasciculations, grand mal convulsion, hyperalgesia, hysteria, manic-depressive reaction, meningitis, myelitis, neuralgia, neuropathy, nystagmus, peripheral neuritis, psychotic depression, psychosis, reflexes decreased, reflexes increased, stupor, torticollis, trismus, withdrawal syndrome.

Respiratory System

Infrequent: Asthma, bronchitis, dyspnea, epistaxis, hyperventilation, pneumonia, respiratory flu; rare: Emphysema, hemoptysis, hiccups, lung fibrosis, pulmonary edema, sputum increased, stridor, voice alteration.

Skin and Appendages

Frequent: Pruritus; infrequent: Acne, alopecia, contact dermatitis, dry skin, ecchymosis, eczema, herpes simplex, photosensitivity, urticaria; rare: Angioedema, erythema nodosum, erythema multiforme, exfoliative dermatitis, fungal dermatitis, furunculosis; herpes zoster, hirsutism, maculopapular rash, seborrhea, skin discoloration, skin hypertrophy, skin ulcer, sweating decreased, vesiculobullous rash.

Special Senses

Frequent: Tinnitus; infrequent: Abnormality of accommodation, conjunctivitis, ear pain, eye pain, keratoconjunctivitis, mydriasis, otitis media; rare: Amblyopia, anisocoria, blepharitis, cataract, conjunctival edema, corneal ulcer, deafness, exophthalmos, eye hemorrhage, glaucoma, hyperacusis, night blindness, otitis externa, parosmia, photophobia, ptosis, retinal hemorrhage, taste loss, visual field defect.

Urogenital System

Infrequent: Amenorrhea, breast pain, cystitis, dysuria, hematuria, menorrhagia, nocturia, polyuria, pyuria, urinary incontinence, urinary retention, urinary urgency, vaginitis; rare: Abortion, breast atrophy, breast enlargement, endometrial disorder, epididymitis, female lactation, fibrocystic breast, kidney calculus, kidney pain, leukorrhea, mastitis, metrorrhagia, nephritis, oliguria, salpingitis, urethritis, urinary casts, uterine spasm, urolith, vaginal hemorrhage, vaginal moniliasis.

Postmarketing Reports

Voluntary reports of adverse events in patients taking PAXIL that have been received since market introduction and not listed above that may have no causal relationship with the drug include acute pancreatitis, elevated liver function tests (the most severe cases were deaths due to liver necrosis, and grossly elevated transaminases associated with severe liver dysfunction), Guillain-Barré syndrome, Stevens-Johnson syndrome, toxic epidermal necrolysis, priapism, syndrome of inappropriate ADH secretion, symptoms suggestive of prolactinemia and galactorrhea; extrapyramidal symptoms which have included akathisia, bradykinesia, cogwheel rigidity, dystonia, hypertonia, oculogyric crisis which has been associated with concomitant use of pimozide; tremor and trismus; status epilepticus, acute renal failure, pulmonary hypertension, allergic alveolitis, anaphylaxis, eclampsia, laryngismus, optic neuritis, porphyria,restless legs syndrome (RLS), ventricular fibrillation, ventricular tachycardia (including torsade de pointes), thrombocytopenia, hemolytic anemia, events related to impaired hematopoiesis (including aplastic anemia, pancytopenia, bone marrow aplasia, and agranulocytosis), and vasculitic syndromes (such as Henoch-Schönlein purpura). There has been a case report of an elevated phenytoin level after 4 weeks of PAXIL and phenytoin coadministration. There has been a case report of severe hypotension when PAXIL was added to chronic metoprolol treatment.

DRUG ABUSE AND DEPENDENCE

Controlled Substance Class

PAXIL is not a controlled substance.

Physical and Psychologic Dependence

PAXIL has not been systematically studied in animals or humans for its potential for abuse, tolerance or physical dependence. While the clinical trials did not reveal any tendency for any drug-seeking behavior, these observations were not systematic and it is not possible to predict on the basis of this limited experience the extent to which a CNS-active drug will be misused, diverted, and/or abused once marketed. Consequently, patients should be evaluated carefully for history of drug abuse, and such patients should be observed closely for signs of misuse or abuse of PAXIL (e.g., development of tolerance, incrementations of dose, drug-seeking behavior).

OVERDOSAGE

Human Experience

Since the introduction of PAXIL in the United States, 342 spontaneous cases of deliberate or accidental overdosage during paroxetine treatment have been reported worldwide (circa 1999). These include overdoses with paroxetine alone and in combination with other substances. Of these, 48 cases were fatal and of the fatalities, 17 appeared to involve paroxetine alone. Eight fatal cases that documented the amount of paroxetine ingested were generally confounded by the ingestion of other drugs or alcohol or the presence of significant comorbid conditions. Of 145 non-fatal cases with known outcome, most recovered without sequelae. The largest known ingestion involved 2,000 mg of paroxetine (33 times the maximum recommended daily dose) in a patient who recovered.

Commonly reported adverse events associated with paroxetine overdosage include somnolence, coma, nausea, tremor, tachycardia, confusion, vomiting, and dizziness. Other notable signs and symptoms observed with overdoses involving paroxetine (alone or with other substances) include mydriasis, convulsions (including status epilepticus), ventricular dysrhythmias (including torsade de pointes), hypertension, aggressive reactions, syncope, hypotension, stupor, bradycardia, dystonia, rhabdomyolysis, symptoms of hepatic dysfunction (including hepatic failure, hepatic necrosis, jaundice, hepatitis, and hepatic steatosis), serotonin syndrome, manic reactions, myoclonus, acute renal failure, and urinary retention.

Overdosage Management

No specific antidotes for paroxetine are known. Treatment should consist of those general measures employed in the management of overdosage with any drugs effective in the treatment of major depressive disorder.

Ensure an adequate airway, oxygenation, and ventilation. Monitor cardiac rhythm and vital signs. General supportive and symptomatic measures are also recommended. Induction of emesis is not recommended.Due to the large volume of distribution of this drug, forced diuresis, dialysis, hemoperfusion, or exchange transfusion are unlikely to be of benefit..

A specific caution involves patients who are taking or have recently taken paroxetine who might ingest excessive quantities of a tricyclic antidepressant. In such a case, accumulation of the parent tricyclic and/or an active metabolite may increase the possibility of clinically significant sequelae and extend the time needed for close medical observation (see PRECAUTIONS: Drugs Metabolized by Cytochrome CYP2D6).

In managing overdosage, consider the possibility of multiple drug involvement. The physician should consider contacting a poison control center for additional information on the treatment of any overdose. Telephone numbers for certified poison control centers are listed in the Physicians' Desk Reference (PDR).

DOSAGE AND ADMINISTRATION

Major Depressive Disorder

Usual Initial Dosage

PAXIL should be administered as a single daily dose with or without food, usually in the morning. The recommended initial dose is 20 mg/day. Patients were dosed in a range of 20 to 50 mg/day in the clinical trials demonstrating the effectiveness of PAXIL in the treatment of major depressive disorder. As with all drugs effective in the treatment of major depressive disorder, the full effect may be delayed. Some patients not responding to a 20-mg dose may benefit from dose increases, in 10-mg/day increments, up to a maximum of 50 mg/day. Dose changes should occur at intervals of at least 1 week.

Maintenance Therapy

There is no body of evidence available to answer the question of how long the patient treated with PAXIL should remain on it. It is generally agreed that acute episodes of major depressive disorder require several months or longer of sustained pharmacologic therapy. Whether the dose needed to induce remission is identical to the dose needed to maintain and/or sustain euthymia is unknown.

Systematic evaluation of the efficacy of PAXIL has shown that efficacy is maintained for periods of up to 1 year with doses that averaged about 30 mg.

Obsessive Compulsive Disorder

Usual Initial Dosage

PAXIL should be administered as a single daily dose with or without food, usually in the morning. The recommended dose of PAXIL in the treatment of OCD is 40 mg daily. Patients should be started on 20 mg/day and the dose can be increased in 10-mg/day increments. Dose changes should occur at intervals of at least 1 week. Patients were dosed in a range of 20 to 60 mg/day in the clinical trials demonstrating the effectiveness of PAXIL in the treatment of OCD. The maximum dosage should not exceed 60 mg/day.

Maintenance Therapy

Long-term maintenance of efficacy was demonstrated in a 6-month relapse prevention trial. In this trial, patients with OCD assigned to paroxetine demonstrated a lower relapse rate compared to patients on placebo (see CLINICAL PHARMACOLOGY: Clinical Trials). OCD is a chronic condition, and it is reasonable to consider continuation for a responding patient. Dosage adjustments should be made to maintain the patient on the lowest effective dosage, and patients should be periodically reassessed to determine the need for continued treatment.

Panic Disorder

Usual Initial Dosage

PAXIL should be administered as a single daily dose with or without food, usually in the morning. The target dose of PAXIL in the treatment of panic disorder is 40 mg/day. Patients should be started on 10 mg/day. Dose changes should occur in 10-mg/day increments and at intervals of at least 1 week. Patients were dosed in a range of 10 to 60 mg/day in the clinical trials demonstrating the effectiveness of PAXIL. The maximum dosage should not exceed 60 mg/day.

Maintenance Therapy

Long-term maintenance of efficacy was demonstrated in a 3-month relapse prevention trial. In this trial, patients with panic disorder assigned to paroxetine demonstrated a lower relapse rate compared to patients on placebo (see CLINICAL PHARMACOLOGY: Clinical Trials). Panic disorder is a chronic condition, and it is reasonable to consider continuation for a responding patient. Dosage adjustments should be made to maintain the patient on the lowest effective dosage, and patients should be periodically reassessed to determine the need for continued treatment.

Social Anxiety Disorder

Usual Initial Dosage

PAXIL should be administered as a single daily dose with or without food, usually in the morning. The recommended and initial dosage is 20 mg/day. In clinical trials the effectiveness of PAXIL was demonstrated in patients dosed in a range of 20 to 60 mg/day. While the safety of PAXIL has been evaluated in patients with social anxiety disorder at doses up to 60 mg/day, available information does not suggest any additional benefit for doses above 20 mg/day (see CLINICAL PHARMACOLOGY: Clinical Trials).

Maintenance Therapy

There is no body of evidence available to answer the question of how long the patient treated with PAXIL should remain on it. Although the efficacy of PAXIL beyond 12 weeks of dosing has not been demonstrated in controlled clinical trials, social anxiety disorder is recognized as a chronic condition, and it is reasonable to consider continuation of treatment for a responding patient. Dosage adjustments should be made to maintain the patient on the lowest effective dosage, and patients should be periodically reassessed to determine the need for continued treatment.

Generalized Anxiety Disorder

Usual Initial Dosage

PAXIL should be administered as a single daily dose with or without food, usually in the morning. In clinical trials the effectiveness of PAXIL was demonstrated in patients dosed in a range of 20 to 50 mg/day. The recommended starting dosage and the established effective dosage is 20 mg/day. There is not sufficient evidence to suggest a greater benefit to doses higher than 20 mg/day. Dose changes should occur in 10 mg/day increments and at intervals of at least 1 week.

Maintenance Therapy

Systematic evaluation of continuing PAXIL for periods of up to 24 weeks in patients with Generalized Anxiety Disorder who had responded while taking PAXIL during an 8-week acute treatment phase has demonstrated a benefit of such maintenance (see CLINICAL PHARMACOLOGY: Clinical Trials). Nevertheless, patients should be periodically reassessed to determine the need for maintenance treatment.

Posttraumatic Stress Disorder

Usual Initial Dosage

PAXIL should be administered as a single daily dose with or without food, usually in the morning. The recommended starting dosage and the established effective dosage is 20 mg/day. In 1 clinical trial, the effectiveness of PAXIL was demonstrated in patients dosed in a range of 20 to 50 mg/day. However, in a fixed dose study, there was not sufficient evidence to suggest a greater benefit for a dose of 40 mg/day compared to 20 mg/day. Dose changes, if indicated, should occur in 10 mg/day increments and at intervals of at least 1 week.

Maintenance Therapy

There is no body of evidence available to answer the question of how long the patient treated with PAXIL should remain on it. Although the efficacy of PAXIL beyond 12 weeks of dosing has not been demonstrated in controlled clinical trials, PTSD is recognized as a chronic condition, and it is reasonable to consider continuation of treatment for a responding patient. Dosage adjustments should be made to maintain the patient on the lowest effective dosage, and patients should be periodically reassessed to determine the need for continued treatment.

Special Populations

Treatment of Pregnant Women During the Third Trimester

Neonates exposed to PAXIL and other SSRIs or SNRIs, late in the third trimester have developed complications requiring prolonged hospitalization, respiratory support, and tube feeding (see WARNINGS: Usage in Pregnancy). When treating pregnant women with paroxetine during the third trimester, the physician should carefully consider the potential risks and benefits of treatment. The physician may consider tapering paroxetine in the third trimester.

Dosage for Elderly or Debilitated Patients, and Patients With Severe Renal or Hepatic Impairment

The recommended initial dose is 10 mg/day for elderly patients, debilitated patients, and/or patients with severe renal or hepatic impairment. Increases may be made if indicated. Dosage should not exceed 40 mg/day.

Switching Patients to or From a Monoamine Oxidase Inhibitor Antidepressant

At least 14 days should elapse between discontinuation of an MAOI intended to treat depression and initiation of therapy with PAXIL. Conversely, at least 14 days should be allowed after stopping PAXIL before starting an MAOI antidepressant (see CONTRAINDICATIONS).

Use of PAXIL With Reversible MAOIs Such as Linezolid or Methylene Blue:Do not start PAXIL in a patient who is being treated with linezolid or methylene blue because there is increased risk of serotonin syndrome or NMS-like reactions. In a patient who requires more urgent treatment of a psychiatric condition, non-pharmacological interventions, including hospitalization, should be considered (see CONTRAINDICATIONS). In some cases, a patient receiving therapy with PAXIL may require urgent treatment with linezolid or methylene blue. If acceptable alternatives to linezolid or methylene blue treatment are not available and the potential benefits of linezolid or methylene blue treatment are judged to outweigh the risks of serotonin syndrome or NMS-like reactions in a particular patient, PAXIL should be stopped promptly, and linezolid or methylene blue can be administered. The patient should be monitored for symptoms of serotonin syndrome or NMS-like reactions for 2 weeks or until 24 hours after the last dose of linezolid or methylene blue, whichever comes first. Therapy with PAXIL may be resumed 24 hours after the last dose of linezolid or methylene blue (see WARNINGS).

Discontinuation of Treatment With PAXIL

Symptoms associated with discontinuation of PAXIL have been reported (see PRECAUTIONS: Discontinuation of Treatment With PAXIL). Patients should be monitored for these symptoms when discontinuing treatment, regardless of the indication for which PAXIL is being prescribed. A gradual reduction in the dose rather than abrupt cessation is recommended whenever possible. If intolerable symptoms occur following a decrease in the dose or upon discontinuation of treatment, then resuming the previously prescribed dose may be considered. Subsequently, the physician may continue decreasing the dose but at a more gradual rate.

NOTE: SHAKE SUSPENSION WELL BEFORE USING.

HOW SUPPLIED

Tablets

Film-coated, modified-oval as follows:

20-mg pink, scored tablets engraved on the front with PAXIL and on the back with 20.

NDC 54868-2976-2 Bottles of 30

NDC 54868-2976-3 Bottles of 60

30-mg blue tablets engraved on the front with PAXIL and on the back with 30.

NDC 54868-3526-0 Bottles of 30

NDC 54868-3526-1 Bottles of 60

Store tablets between 15° and 30°C (59° and 86°F).

PAXIL is a registered trademark of GlaxoSmithKline.

GlaxoSmithKline

Research Triangle Park, NC 27709

©2011, GlaxoSmithKline. All rights reserved.

July 2011 PXL:59PI

Relabeling and Repackaging by:

Physicians Total Care, Inc.

Tulsa, Oklahoma 74146

Medication Guide

PAXIL® (PAX-il)

(paroxetine hydrochloride)

Tablets and Oral Suspension

Read the Medication Guide that comes with PAXIL before you start taking it and each time you get a refill. There may be new information. This Medication Guide does not take the place of talking to your healthcare provider about your medical condition or treatment. Talk with your healthcare provider if there is something you do not understand or want to learn more about.

What is the most important information I should know about PAXIL?

PAXIL and other antidepressant medicines may cause serious side effects, including:

1. Suicidal thoughts or actions:

- PAXIL and other antidepressant medicines may increase suicidal thoughts or actions in some children, teenagers, or young adults within the first few months of treatment or when the dose is changed.
- Depression or other serious mental illnesses are the most important causes of suicidal thoughts or actions.
- Watch for these changes and call your healthcare provider right away if you notice:
  - New or sudden changes in mood, behavior, actions, thoughts, or feelings, especially if severe.
  - Pay particular attention to such changes when PAXIL is started or when the dose is changed.

Keep all follow-up visits with your healthcare provider and call between visits if you are worried about symptoms.

Call your healthcare provider right away if you have any of the following symptoms, or call 911 if an emergency, especially if they are new, worse, or worry you:

- attempts to commit suicide
- acting on dangerous impulses
- acting aggressive or violent
- thoughts about suicide or dying
- new or worse depression
- new or worse anxiety or panic attacks
- feeling agitated, restless, angry, or irritable
- trouble sleeping
- an increase in activity or talking more than what is normal for you
- other unusual changes in behavior or mood

Call your healthcare provider right away if you have any of the following symptoms, or call 911 if an emergency. PAXIL may be associated with these serious side effects:

2. Serotonin Syndrome or Neuroleptic Malignant Syndrome-like reactions. This condition can be life-threatening and may include:

- agitation, hallucinations, coma, or other changes in mental status
- coordination problems or muscle twitching (overactive reflexes)
- racing heartbeat, high or low blood pressure
- sweating or fever
- nausea, vomiting, or diarrhea
- muscle rigidity

3. Severe allergic reactions:

- trouble breathing
- swelling of the face, tongue, eyes, or mouth
- rash, itchy welts (hives), or blisters, alone or with fever or joint pain

4. Abnormal bleeding: PAXIL and other antidepressant medicines may increase your risk of bleeding or bruising, especially if you take the blood thinner warfarin (Coumadin®, Jantoven®), a non-steroidal anti-inflammatory drug (NSAIDs, like ibuprofen or naproxen), or aspirin.

5. Seizures or convulsions

6. Manic episodes:

- greatly increased energy
- severe trouble sleeping
- racing thoughts
- reckless behavior
- unusually grand ideas
- excessive happiness or irritability
- talking more or faster than usual

7. Changes in appetite or weight. Children and adolescents should have height and weight monitored during treatment.

8. Low salt (sodium) levels in the blood. Elderly people may be at greater risk for this. Symptoms may include:

- headache
- weakness or feeling unsteady
- confusion, problems concentrating or thinking, or memory problems

Do not stop PAXIL without first talking to your healthcare provider. Stopping PAXIL too quickly may cause serious symptoms including:

- anxiety, irritability, high or low mood, feeling restless, or changes in sleep habits
- headache, sweating, nausea, dizziness
- electric shock-like sensations, shaking, confusion

What is PAXIL?

PAXIL is a prescription medicine used to treat depression. It is important to talk with your healthcare provider about the risks of treating depression and also the risks of not treating it. You should discuss all treatment choices with your healthcare provider. PAXIL is also used to treat:

- Major Depressive Disorder (MDD)
- Obsessive Compulsive Disorder (OCD)
- Panic Disorder
- Social Anxiety Disorder
- Generalized Anxiety Disorder (GAD)
- Posttraumatic Stress Disorder (PTSD)

Talk to your healthcare provider if you do not think that your condition is getting better with treatment using PAXIL.

Who should not take PAXIL?

Do not take PAXIL if you:

- are allergic to paroxetine or any of the ingredients in PAXIL. See the end of this Medication Guide for a complete list of ingredients in PAXIL.
- take a monoamine oxidase inhibitor (MAOI). Ask your healthcare provider or pharmacist if you are not sure if you take an MAOI, including the antibiotic linezolid.
- Do not take an MAOI within 2 weeks of stopping PAXIL unless directed to do so by your physician.
- Do not start PAXIL if you stopped taking an MAOI in the last 2 weeks unless directed to do so by your physician.
- People who take PAXIL close in time to an MAOI may have serious or even life-threatening side effects. Get medical help right away if you have any of these symptoms:
  - high fever
  - uncontrolled muscle spasms
  - stiff muscles
  - rapid changes in heart rate or blood pressure
  - confusion
  - loss of consciousness (pass out)

- take MELLARIL® (thioridazine). Do not take MELLARIL® together with PAXIL because this can cause serious heart rhythm problems or sudden death.
- take the antipsychotic medicine pimozide (ORAP®) because this can cause serious heart problems.

What should I tell my healthcare provider before taking PAXIL? Ask if you are not sure.

Before starting PAXIL, tell your healthcare provider if you:

- are pregnant, may be pregnant, or plan to become pregnant. There is a possibility that PAXIL may harm your unborn baby, including an increased risk of birth defects, particularly heart defects. Other risks may include a serious condition in which there is not enough oxygen in the baby’s blood. Your baby may also have certain other symptoms shortly after birth. Premature births have also been reported in some women who used PAXIL during pregnancy
- are breastfeeding. PAXIL passes into your milk. Talk to your healthcare provider about the best way to feed your baby while taking PAXIL.
- are taking certain drugs such as:
  - triptans used to treat migraine headache
  - other antidepressants (SSRIs, SNRIs, tricyclics, or lithium) or antipsychotics
  - drugs that affect serotonin, such as lithium, tramadol, tryptophan, St. John’s wort
  - certain drugs used to treat irregular heart beats
  - certain drugs used to treat schizophrenia
  - certain drugs used to treat HIV infection
  - certain drugs that affect the blood, such as warfarin, aspirin, and ibuprofen
  - certain drugs used to treat epilepsy
  - atomoxetine
  - cimetidine
  - fentanyl
  - metoprolol
  - pimozide
  - procyclidine
  - tamoxifen
- have liver problems
- have kidney problems
- have heart problems
- have or had seizures or convulsions
- have bipolar disorder or mania
- have low sodium levels in your blood
- have a history of a stroke
- have high blood pressure
- have or had bleeding problems
- have glaucoma (high pressure in the eye)

Tell your healthcare provider about all the medicines you take, including prescription and non-prescription medicines, vitamins, and herbal supplements. PAXIL and some medicines may interact with each other, may not work as well, or may cause serious side effects.

Your healthcare provider or pharmacist can tell you if it is safe to take PAXIL with your other medicines. Do not start or stop any medicine while taking PAXIL without talking to your healthcare provider first.

BOXED WARNING

If you take PAXIL, you should not take any other medicines that contain paroxetine, including PAXIL CR and PEXEVA® (paroxetine mesylate).

How should I take PAXIL?

- Take PAXIL exactly as prescribed. Your healthcare provider may need to change the dose of PAXIL until it is the right dose for you.
- PAXIL may be taken with or without food.
- If you are taking PAXIL Oral Suspension, shake the suspension well before use.
- If you miss a dose of PAXIL, take the missed dose as soon as you remember. If it is almost time for the next dose, skip the missed dose and take your next dose at the regular time. Do not take two doses of PAXIL at the same time.
- If you take too much PAXIL, call your healthcare provider or poison control center right away, or get emergency treatment.
- Do not stop taking PAXIL suddenly without talking to your doctor (unless you have symptoms of a severe allergic reaction). If you need to stop taking PAXIL, your healthcare provider can tell you how to safely stop taking it.

What should I avoid while taking PAXIL?

PAXIL can cause sleepiness or may affect your ability to make decisions, think clearly, or react quickly. You should not drive, operate heavy machinery, or do other dangerous activities until you know how PAXIL affects you. Do not drink alcohol while using PAXIL.

What are possible side effects of PAXIL?

PAXIL may cause serious side effects, including all of those described in the section entitled “What is the most important information I should know about PAXIL?”

Common possible side effects in people who take PAXIL include:

- nausea
- sleepiness
- weakness
- dizziness
- feeling anxious or trouble sleeping
- sexual problems
- sweating
- shaking
- not feeling hungry
- dry mouth
- constipation
- infection
- yawning

Tell your healthcare provider if you have any side effect that bothers you or that does not go away. These are not all the possible side effects of PAXIL. For more information, ask your healthcare provider or pharmacist.

CALL YOUR DOCTOR FOR MEDICAL ADVICE ABOUT SIDE EFFECTS. YOU MAY REPORT SIDE EFFECTS TO THE FDA AT 1-800-FDA-1088 or 1-800-332-1088.

How should I store PAXIL?

- Store PAXIL Tablets at room temperature between 59º and 86ºF (15º and 30ºC).
- Store PAXIL Oral Suspension at or below 77ºF (25ºC).
- Keep PAXIL away from light.
- Keep bottle of PAXIL closed tightly.

Keep PAXIL and all medicines out of the reach of children.

General information about PAXIL

Medicines are sometimes prescribed for purposes other than those listed in a Medication Guide. Do not use PAXIL for a condition for which it was not prescribed. Do not give PAXIL to other people, even if they have the same condition. It may harm them.

This Medication Guide summarizes the most important information about PAXIL. If you would like more information, talk with your healthcare provider. You may ask your healthcare provider or pharmacist for information about PAXIL that is written for healthcare professionals.

For more information about PAXIL call 1-888-825-5249 or go to www.us.gsk.com.

What are the ingredients in PAXIL?

Active ingredient: paroxetine hydrochloride

Inactive ingredients in tablets: dibasic calcium phosphate dihydrate, hypromellose, magnesium stearate, polyethylene glycols, polysorbate 80, sodium starch glycolate, titanium dioxide, and 1 or more of the following: D&C Red No. 30 aluminum lake, D&C Yellow No. 10 aluminum lake, FD&C Blue No. 2 aluminum lake, FD&C Yellow No. 6 aluminum lake.

Inactive ingredients in suspension for oral administration: polacrilin potassium, microcrystalline cellulose, propylene glycol, glycerin, sorbitol, methylparaben, propylparaben, sodium citrate dihydrate, citric acid anhydrous, sodium saccharin, flavorings, FD&C Yellow No. 6 aluminum lake, and simethicone emulsion, USP.

PAXIL and PAXIL CR are registered trademarks of GlaxoSmithKline. The other brands listed are trademarks of their respective owners and are not trademarks of GlaxoSmithKline. The makers of these brands are not affiliated with and do not endorse GlaxoSmithKline or its products.

This Medication Guide has been approved by the U.S. Food and Drug Administration.

GlaxoSmithKline

Research Triangle Park, NC 27709

©2011, GlaxoSmithKline. All rights reserved.

July 2011 PXL:6MG

Principal Display Panel

PAXIL®

PAROXETINE HCl TABLETS

20 mg

Rx only

Federal Law requires dispensing of Paxil® with the Medication Guide under this label.

Store tablets between 15o and 30oC (59o and 86oF). Dispense in a tight, light-resistant container. Each tablet contains paroxetine hydrochloride equivalent to 20 mg paroxetine.

Dosage: See accompanying prescribing information.

Important: Use safety closures when dispensing this product unless otherwise directed by physician or requested by purchaser.

Principal Display Panel

PAXIL®

PAROXETINE HCl TABLETS

30 mg

Rx only

Federal Law requires dispensing of Paxil® with the Medication Guide under this label.

Store tablets between 15o and 30oC (59o and 86oF). Dispense in a tight, light-resistant container. Each tablet contains paroxetine hydrochloride equivalent to 30 mg paroxetine.

Dosage: See accompanying prescribing information.

Important: Use safety closures when dispensing this product unless otherwise directed by physician or requested by purchaser.